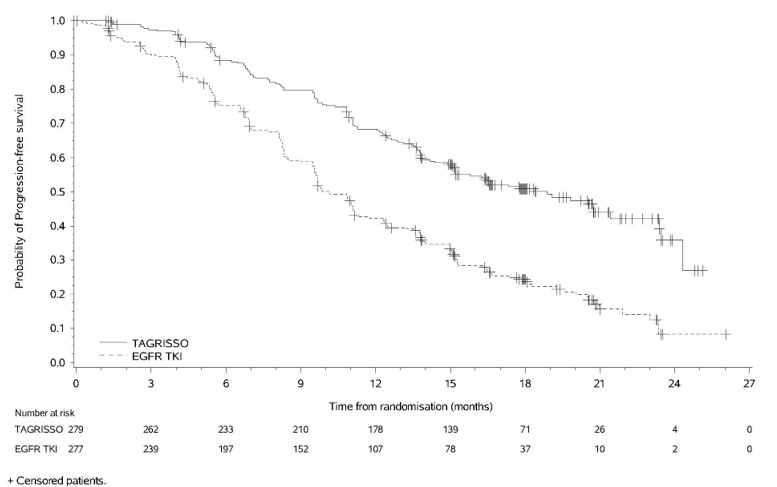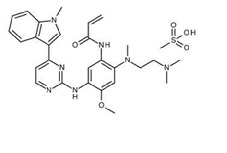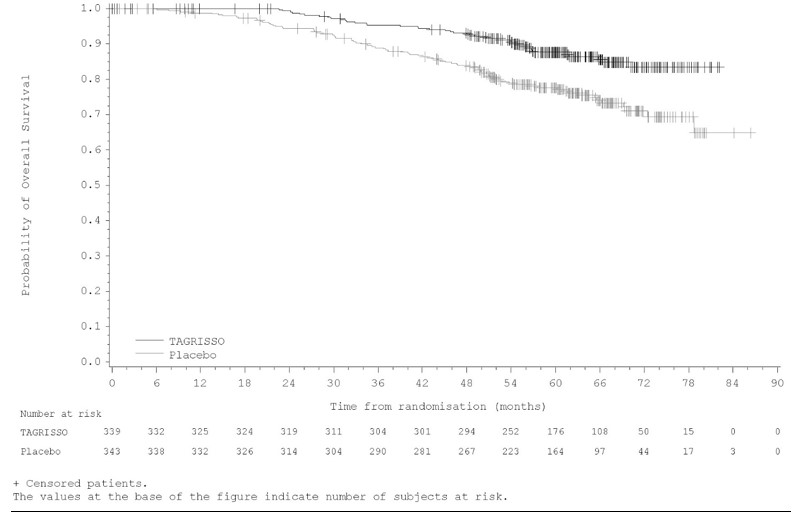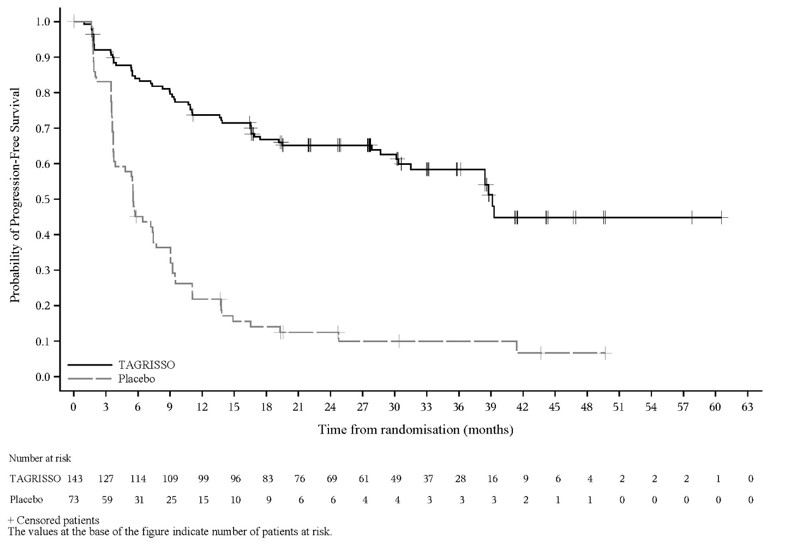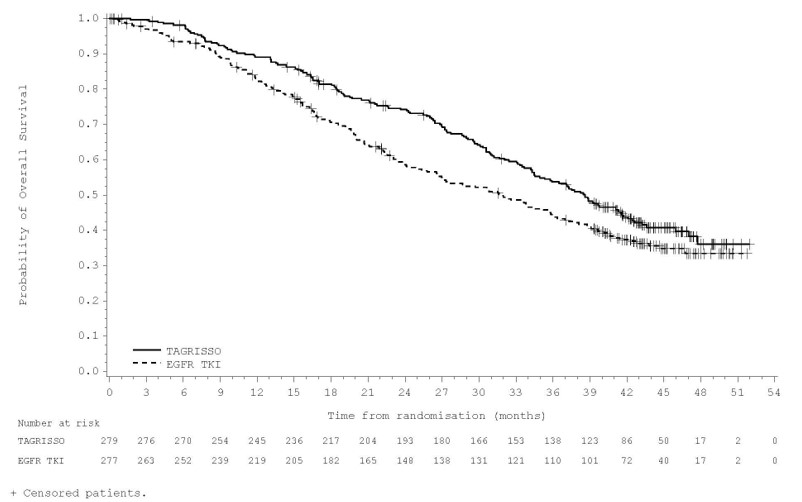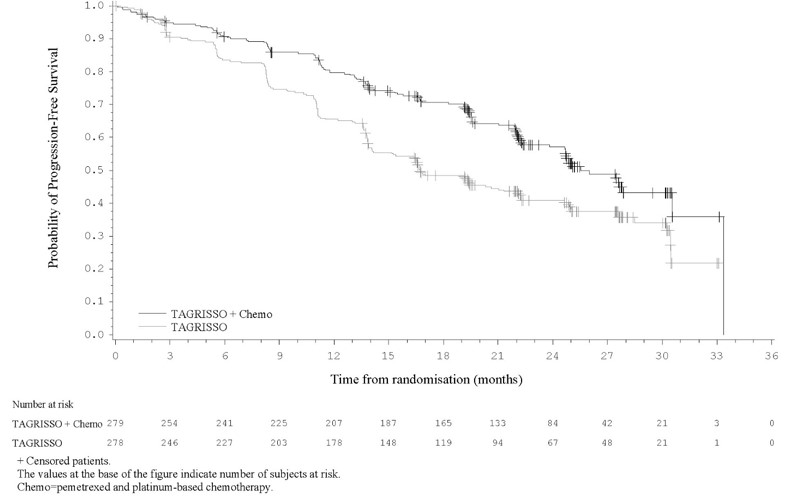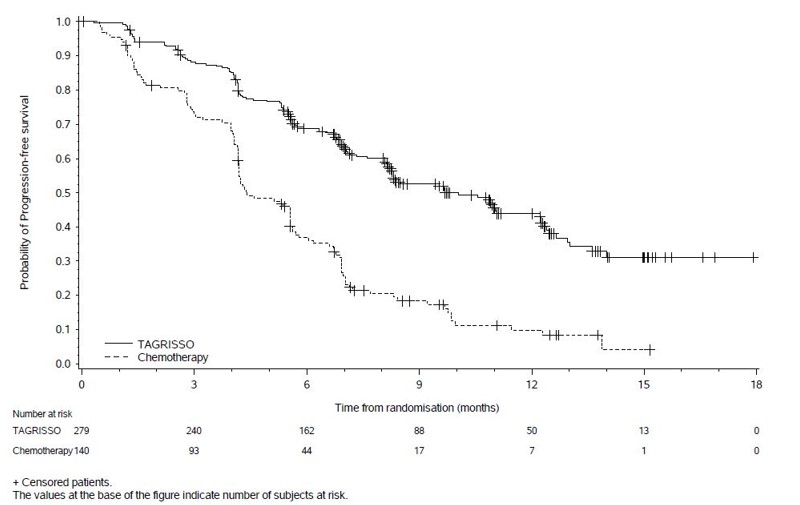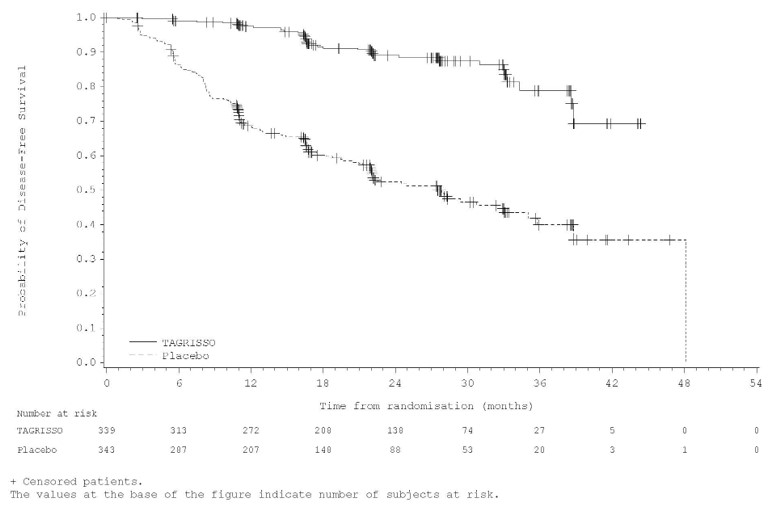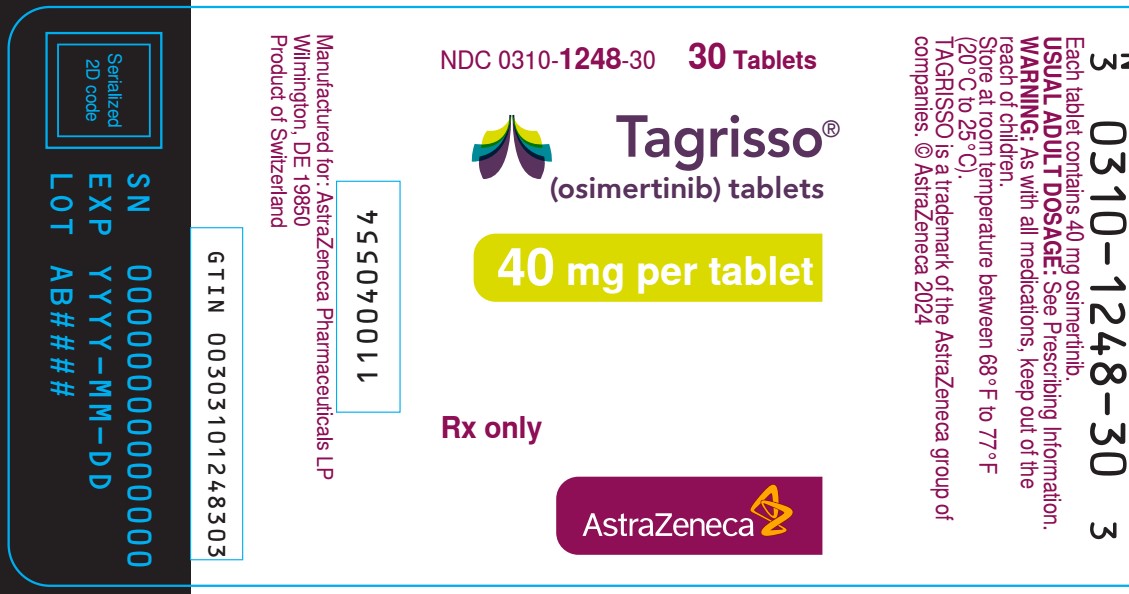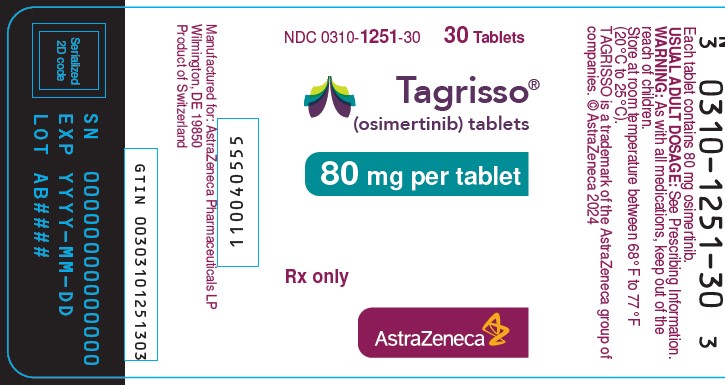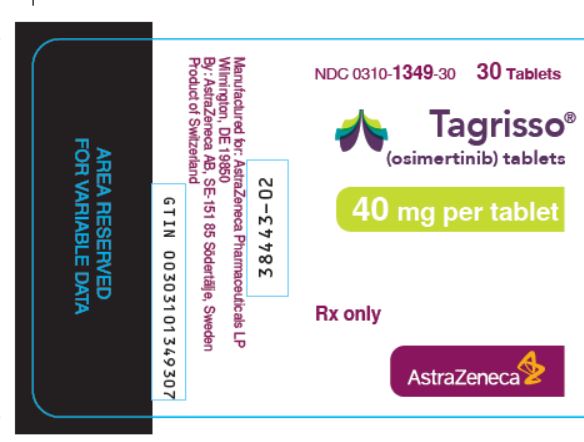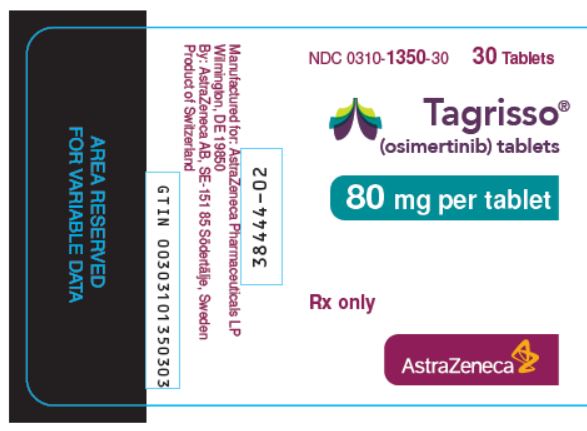 DRUG LABEL: TAGRISSO
NDC: 0310-1349 | Form: TABLET, FILM COATED
Manufacturer: AstraZeneca Pharmaceuticals LP
Category: prescription | Type: HUMAN PRESCRIPTION DRUG LABEL
Date: 20240925

ACTIVE INGREDIENTS: OSIMERTINIB 40 mg/1 1
INACTIVE INGREDIENTS: MANNITOL; MICROCRYSTALLINE CELLULOSE; SODIUM STEARYL FUMARATE; POLYVINYL ALCOHOL, UNSPECIFIED; TITANIUM DIOXIDE; POLYETHYLENE GLYCOL 3350; TALC; FERRIC OXIDE YELLOW; FERRIC OXIDE RED; FERROSOFERRIC OXIDE; LOW-SUBSTITUTED HYDROXYPROPYL CELLULOSE, UNSPECIFIED

HIGHLIGHTS OF PRESCRIBING INFORMATION

These highlights do not include all the information needed to use TAGRISSO safely and effectively. See full prescribing information for TAGRISSO.
TAGRISSO® (osimertinib) tablets, for oral use
Initial U.S. Approval: 2015

RECENT MAJOR CHANGES

Indications and Usage (1.2) 09/2024

Indications and Usage (1.4) 02/2024

Dosage and Administration, Patient Selection (2.2) 09/2024

Dosage and Administration, Recommended Dosage

and Administration (2.3) 09/2024

Dosage and Administration, Dosage Modifications (2.5) 09/2024

Warnings and Precautions, Interstitial Lung

Disease/Pneumonitis (Error! Hyperlink reference not valid.) 09/2024

Warnings and Precautions, QTc Interval Prolongation (Error! Hyperlink reference not valid.) 09/2024

Warnings and Precautions, Cardiomyopathy (Error! Hyperlink reference not valid.) 09/2024

Warnings and Precautions, Keratitis (Error! Hyperlink reference not valid.) 09/2024

Warnings and Precautions, Aplastic Anemia (Error! Hyperlink reference not valid.) 02/2024

1 INDICATIONS AND USAGE

TAGRISSO is a kinase inhibitor indicated for:

- adjuvant therapy after tumor resection in adult patients with non-small cell lung cancer (NSCLC) whose tumors have epidermal growth factor receptor (EGFR) exon 19 deletions or exon 21 L858R mutations, as detected by an FDA-approved test. (1.1, 2.2)
- the treatment of adult patients with locally advanced, unresectable (stage III) NSCLC whose disease has not progressed during or following concurrent or sequential platinum-based chemoradiation therapy and whose tumors have EGFR exon 19 deletions or exon 21 L858R mutations, as detected by an FDA-approved test. (1.2, 2.2)
- the first-line treatment of adult patients with metastatic NSCLC whose tumors have EGFR exon 19 deletions or exon 21 L858R mutations, as detected by an FDA-approved test. (1.3, 2.2)
- in combination with pemetrexed and platinum-based chemotherapy, the first-line treatment of adult patients with locally advanced or metastatic NSCLC whose tumors have EGFR exon 19 deletions or exon 21 L858R mutations, as detected by an FDA-approved test. (1.4, 2.2)
- the treatment of adult patients with metastatic EGFR T790M mutation-positive NSCLC, as detected by an FDA-approved test, whose disease has progressed on or after EGFR TKI therapy. (1.5, 2.2)

2 DOSAGE AND ADMINISTRATION

Adjuvant treatment of early-stage NSCLC: 80 mg orally once daily, with or without food, until disease recurrence, or unacceptable toxicity, or for up to 3 years. (2.3)

Locally advanced, unresectable (stage III) NSCLC: Following platinum-based chemoradiation therapy, 80 mg orally once daily, with or without food, until disease progression or unacceptable toxicity. (2.3)

Metastatic NSCLC: 80 mg orally once daily, with or without food, until disease progression or unacceptable toxicity. (2.3)

Locally advanced or metastatic NSCLC: 80 mg orally once daily administered in combination with pemetrexed and platinum-based chemotherapy, with or without food, until disease progression or unacceptable toxicity due to TAGRISSO. (2.3)

3 DOSAGE FORMS AND STRENGTHS

Tablets: 80 mg and 40 mg. (3)

4 CONTRAINDICATIONS

None. (4)

5 WARNINGS AND PRECAUTIONS

- Interstitial Lung Disease (ILD)/Pneumonitis: Monitor for new or worsening pulmonary symptoms indicative of ILD/pneumonitis. For patients receiving TAGRISSO who have not received recent definite platinum-based chemoradiation therapy, permanently discontinue TAGRISSO in patients diagnosed with ILD/Pneumonitis. For patients who received recent definitive platinum-based chemoradiation therapy with Grade 1 ILD/pneumonitis continue TAGRISSO or interrupt and restart, as appropriate. Permanently discontinue TAGRISSO in patients diagnosed with Grade ≥2 ILD/pneumonitis. (2.5, Error! Hyperlink reference not valid.)
- QTc Interval Prolongation: Monitor electrocardiograms and electrolytes in patients who have a history or predisposition for QTc prolongation, or those who are taking medications that are known to prolong the QTc interval. Withhold, then restart at a reduced dose or permanently discontinue TAGRISSO based on severity. (2.5, Error! Hyperlink reference not valid.)
- Cardiomyopathy: Occurred in 3.8% of patients. Conduct cardiac monitoring, including left ventricular ejection fraction (LVEF) assessment in patients with cardiac risk factors. (2.5, Error! Hyperlink reference not valid.)
- Keratitis: Promptly refer patients with signs and symptoms of keratitis to an ophthalmologist for evaluation. (Error! Hyperlink reference not valid.)
- Erythema Multiforme Major, Stevens-Johnson Syndrome, and Toxic Epidermal Necrolysis: Withhold TAGRISSO if erythema multiforme major (EMM), Stevens-Johnson syndrome (SJS), or toxic epidermal necrolysis (TEN) is suspected and permanently discontinue if confirmed. (2.5, Error! Hyperlink reference not valid.)
- Cutaneous Vasculitis: Withhold TAGRISSO if cutaneous vasculitis is suspected, evaluate for systemic involvement, and consider dermatology consultation. If no other etiology can be identified, consider permanent discontinuation based on severity. (Error! Hyperlink reference not valid.)
- Aplastic Anemia: Withhold TAGRISSO if aplastic anemia is suspected and permanently discontinue TAGRISSO if confirmed. (2.5, Error! Hyperlink reference not valid.)
- Embryo-Fetal Toxicity: TAGRISSO can cause fetal harm. Advise females of potential risk to the fetus and to use effective contraception during treatment with TAGRISSO and for 6 weeks after last dose. Advise males to use effective contraception for 4 months after the last dose of TAGRISSO. (Error! Hyperlink reference not valid., 8.1, 8.3)

6 ADVERSE REACTIONS

Most common (≥20%) adverse reactions, including laboratory abnormalities, were:

- TAGRISSO monotherapy: leukopenia, lymphopenia, thrombocytopenia, anemia, diarrhea, rash, musculoskeletal pain, neutropenia, nail toxicity, dry skin, stomatitis, and fatigue. (6.1)
- TAGRISSO monotherapy following platinum-based chemoradiation therapy: lymphopenia, leukopenia, ILD/pneumonitis, thrombocytopenia, neutropenia, rash, diarrhea, nail toxicity, musculoskeletal pain, cough and COVID-19. (6.1)
- TAGRISSO in combination with pemetrexed and platinum-based chemotherapy: leukopenia, thrombocytopenia, neutropenia, lymphopenia, rash, diarrhea, stomatitis, nail toxicity, dry skin, and increased blood creatinine. (6.1)

To report SUSPECTED ADVERSE REACTIONS, contact AstraZeneca at 1-800-236-9933 or www.TAGRISSO.com or FDA at 1-800-FDA-1088 or www.fda.gov/medwatch.

7 DRUG INTERACTIONS

Strong CYP3A Inducers: Avoid concomitant use. If not possible, increase TAGRISSO to 160 mg daily in patients receiving a strong CYP3A4 inducer. (2.5, 7.1)

8 USE IN SPECIFIC POPULATIONS

Lactation: Do not breastfeed. (8.2)

FULL PRESCRIBING INFORMATION

1 INDICATIONS AND USAGE

1.1 Adjuvant Treatment of EGFR Mutation-Positive Non-Small Cell Lung Cancer (NSCLC)

TAGRISSO is indicated as adjuvant therapy after tumor resection in adult patients with non-small cell lung cancer (NSCLC) whose tumors have epidermal growth factor receptor (EGFR) exon 19 deletions or exon 21 L858R mutations, as detected by an FDA-approved test [see Dosage and Administration (2.2)].

1.2 Locally Advanced, Unresectable (Stage III) EGFR Mutation-Positive NSCLC

TAGRISSO is indicated for the treatment of adult patients with locally advanced, unresectable (stage III) NSCLC whose disease has not progressed during or following concurrent or sequential platinum-based chemoradiation therapy and whose tumors have EGFR exon 19 deletions or exon 21 L858R mutations, as detected by an FDA-approved test [see Dosage and Administration (2.2)].

1.3 First-line Treatment of EGFR Mutation-Positive Metastatic NSCLC

TAGRISSO is indicated for the first-line treatment of adult patients with metastatic NSCLC whose tumors have EGFR exon 19 deletions or exon 21 L858R mutations, as detected by an FDA-approved test [see Dosage and Administration (2.2)].

1.4 First-line Treatment of EGFR Mutation-Positive Locally Advanced or Metastatic NSCLC

TAGRISSO in combination with pemetrexed and platinum-based chemotherapy is indicated for the first-line treatment of adult patients with locally advanced or metastatic NSCLC whose tumors have EGFR exon 19 deletions or exon 21 L858R mutations, as detected by an FDA-approved test [see Dosage and Administration (2.2)].

1.5 Previously Treated EGFR T790M Mutation-Positive Metastatic NSCLC

TAGRISSO is indicated for the treatment of adult patients with metastatic EGFR T790M mutation-positive NSCLC, as detected by an FDA-approved test, whose disease has progressed on or after EGFR tyrosine kinase inhibitor (TKI) therapy [see Dosage and Administration (2.2)].

2 DOSAGE AND ADMINISTRATION

2.1 Recommended Evaluation and Testing Before Initiating TAGRISSO

TAGRISSO Monotherapy

- Before initiating TAGRISSO monotherapy in patients with cardiac risk factors, conduct cardiac monitoring, including assessment of left ventricular ejection fraction (LVEF) [see Error! Hyperlink reference not valid.].
- Before initiating TAGRISSO, perform complete blood count with differential [see Error! Hyperlink reference not valid.].

TAGRISSO in Combination with Pemetrexed and Platinum-based Chemotherapy

- Before initiating TAGRISSO in combination with pemetrexed and platinum-based chemotherapy, conduct cardiac monitoring in all patients, including assessment of left ventricular ejection fraction (LVEF) [see Error! Hyperlink reference not valid.].
- Before initiating TAGRISSO, perform complete blood count with differential [see Error! Hyperlink reference not valid.].

2.2 Patient Selection

Table 1 below presents the patient selection criteria for treatment with TAGRISSO.

Table : Patient Selection
Select patients for treatment with TAGRISSO based on the presence of a mutation as detected by an FDA-approved test.
Indication | Treatment Regimen | Required Mutation | Source for Testing
Adjuvant Treatment of EGFR Mutation-Positive NSCLC [see Indications and Usage (1.1)] | TAGRISSO monotherapy | EGFR exon 19 deletions or exon 21 L858R mutations | Tumor
Locally Advanced, Unresectable (Stage III) EGFR Mutation-Positive NSCLC [see Indications and Usage (1.2)] | Following completion of platinum-based chemoradiation therapy, TAGRISSO monotherapy | EGFR exon 19 deletions or exon 21 L858R mutations | Tumor
First-line Treatment of EGFR Mutation-Positive Metastatic NSCLC [see Indications and Usage (1.3)] | TAGRISSO monotherapy | EGFR exon 19 deletions or exon 21 L858R mutations | Plasma or tumor
First-line Treatment of EGFR Mutation-Positive Locally Advanced or Metastatic NSCLC [see Indications and Usage (1.4)] | TAGRISSO in combination with pemetrexed and platinum-based chemotherapy | EGFR exon 19 deletions or exon 21 L858R mutations | Plasma or tumor
Previously Treated EGFR T790M Mutation-Positive Metastatic NSCLC [see Indications and Usage (1.5)] | TAGRISSO monotherapy | EGFR T790M Mutation | Plasma or tumor
Information on FDA-approved tests for the detection of EGFR mutations is available at http://www.fda.gov/companiondiagnostics.

2.3 Recommended Dosage and Administration

Recommended Dosage

Table 2 provides the recommended dosage of TAGRISSO by indication.

Table 2. Recommended Dosage of TAGRISSO
Indication | Recommended Dosage of TAGRISSO | Duration of Treatment
Adjuvant Treatment of EGFR Mutation-Positive NSCLC | 80 mg tablet orally once daily with or without food | For a total of 3 years or until disease recurrence or unacceptable toxicity
Locally Advanced, Unresectable (Stage III) EGFR Mutation-Positive NSCLC | Following platinum-based chemoradiation therapy, 80 mg tablet orally once daily with or without food | Until disease progression or unacceptable toxicity
First-line Treatment of EGFR Mutation-Positive Metastatic NSCLC | 80 mg tablet orally once daily with or without food | Until disease progression or unacceptable toxicity
First-line Treatment of EGFR Mutation-Positive Locally Advanced or Metastatic NSCLC | 80 mg tablet orally once daily with or without food in combination with pemetrexed and platinum-based chemotherapy; Refer to the Prescribing Information for pemetrexed and cisplatin or carboplatin for the respective dosing information. | Until disease progression or unacceptable toxicity due to TAGRISSO
Previously Treated EGFR T790M Mutation-Positive Metastatic NSCLC | 80 mg tablet orally once daily with or without food | Until disease progression or unacceptable toxicity

Administration

Administer TAGRISSO 80 mg tablet orally once daily with or without food. Tablets may be dispersed in water for patients who have difficulty swallowing, or for nasogastric tube administration [see Dosage and Administration (2.4)].

Missed Dose

If a dose of TAGRISSO is missed, do not make up the missed dose and take the next dose as scheduled.

2.4 Administration to Patients Who Have Difficulty Swallowing Solids

Disperse TAGRISSO tablet in 60 mL (2 ounces) of non-carbonated water only. Stir until tablet is dispersed into small pieces (the tablet will not completely dissolve) and swallow immediately. Do not crush, heat, or ultrasonicate during preparation. Rinse the container with 120 mL to 240 mL (4 to 8 ounces) of water and immediately drink.

If administration via nasogastric tube is required, disperse the TAGRISSO tablet as above in 15 mL of non-carbonated water, and then use an additional 15 mL of water to transfer any residues to the syringe. The resulting 30 mL liquid should be administered as per the nasogastric tube instructions with appropriate water flushes (approximately 30 mL). Repeat this step until no pieces remain in the syringe. This will help to ensure that the full prescribed dose of the TAGRISSO is given. The dispersion and residues should be administered within 30 minutes of the addition of the tablets to water.

2.5 Dosage Modifications for Adverse Reactions

The recommended dose reductions for adverse reactions are provided in Table 3.

Table 3. Recommended Dosage Modifications for TAGRISSO
Target Organ | Adverse Reaction [Adverse reactions graded by the National Cancer Institute Common Terminology Criteria for Adverse Events version 5.0 (NCI CTCAE v5.0).] | Dosage Modification
Pulmonary; (Patients who have not received recent definitive platinum-based chemoradiation therapy) [see Error! Hyperlink reference not valid.] | Any Grade; Interstitial lung disease (ILD)/Pneumonitis | Permanently discontinue TAGRISSO.
Pulmonary; (Patients who have received recent definitive platinum-based chemoradiation therapy) [see Error! Hyperlink reference not valid.] | Grade 1; ILD/Pneumonitis | Withhold or continue TAGRISSO, as clinically indicated.
Pulmonary; (Patients who have received recent definitive platinum-based chemoradiation therapy) [see Error! Hyperlink reference not valid.] | Grade ≥2; ILD/Pneumonitis | Permanently discontinue TAGRISSO.
Cardiac; [see Error! Hyperlink reference not valid.2, Error! Hyperlink reference not valid.] | QTc [QTc = QT interval corrected for heart rate] interval greater than 500 msec on at least 2 separate ECGs [ECGs = Electrocardiograms] | Withhold TAGRISSO until QTc interval is less than 481 msec or recovery to baseline if baseline QTc is greater than or equal to 481 msec, then resume at 40 mg dose.
Cardiac; [see Error! Hyperlink reference not valid.2, Error! Hyperlink reference not valid.] | QTc interval prolongation with signs/symptoms of life-threatening arrhythmia | Permanently discontinue TAGRISSO.
Cardiac; [see Error! Hyperlink reference not valid.2, Error! Hyperlink reference not valid.] | Symptomatic congestive heart failure | Permanently discontinue TAGRISSO.
Cutaneous; [see Error! Hyperlink reference not valid.] | Erythema Multiforme Major (EMM), Stevens-Johnson syndrome (SJS), and Toxic Epidermal Necrolysis (TEN) | Withhold TAGRISSO if suspected and permanently discontinue if confirmed.
Blood and bone marrow [see Error! Hyperlink reference not valid.] | Aplastic anemia | Withhold TAGRISSO if aplastic anemia is suspected and permanently discontinue if confirmed.
Other [see Adverse Reactions (6.1)] | Adverse reaction of Grade 3 or greater severity | Withhold TAGRISSO for up to 3 weeks.
Other [see Adverse Reactions (6.1)] | If improvement to Grade 0-2 within 3 weeks | Resume at 80 mg or 40 mg daily.
Other [see Adverse Reactions (6.1)] | If no improvement within 3 weeks | Permanently discontinue TAGRISSO.

Dosage Modifications for Combination Therapy

When TAGRISSO is administered in combination with pemetrexed and platinum-based chemotherapy, modify the dose of any one of the treatments for the management of adverse reactions, as appropriate. For TAGRISSO dose modification instructions, see Table 3. Withhold, reduce the dose or permanently discontinue pemetrexed, cisplatin or carboplatin according to their respective Prescribing Information.

Drug Interactions

Strong CYP3A4 Inducers
Avoid concomitant use of strong CYP3A4 inducers with TAGRISSO. If concurrent use is unavoidable, increase TAGRISSO dosage to 160 mg daily when co-administering with a strong CYP3A inducer. Resume TAGRISSO at 80 mg 3 weeks after discontinuation of the strong CYP3A4 inducer [see Drug Interactions (7) and Clinical Pharmacology (12.3)].

3 DOSAGE FORMS AND STRENGTHS

80 mg tablets: beige, oval and biconvex tablet marked with “AZ 80” on one side and plain on the reverse.

40 mg tablets: beige, round and biconvex tablet marked with “AZ 40” on one side and plain on the reverse.

4 CONTRAINDICATIONS

None.

5 WARNINGS AND PRECAUTIONS

5.1 Interstitial Lung Disease/Pneumonitis

TAGRISSO can cause severe and fatal ILD/pneumonitis.

Across clinical trials, interstitial lung disease (ILD)/pneumonitis occurred in 4% of the 1813 patients treated with TAGRISSO monotherapy who had not received recent definitive chemoradiation therapy; 0.4% of cases were fatal.

ILD/Pneumonitis with TAGRISSO in Combination with Pemetrexed and Platinum-based Chemotherapy

In the FLAURA2 study, ILD/pneumonitis occurred in 3.3% of the 276 patients who received TAGRISSO in combination with pemetrexed and platinum-based chemotherapy; 0.4% of cases were fatal.

ILD/Pneumonitis Following Definitive Platinum-based Chemoradiation Therapy

In the LAURA study, following definitive platinum-based chemoradiation therapy, ILD/pneumonitis, including radiation pneumonitis, occurred in 80 of the 143 patients (56%) who received TAGRISSO monotherapy and 28 of the 73 patients (38%) who received placebo. There was one fatal case (0.7%), 3.5% Grade 3, 34% Grade 2, and 18% Grade 1 adverse reactions of ILD/pneumonitis in TAGRISSO-treated patients. For TAGRISSO-treated patients, ILD/pneumonitis led to permanent discontinuation of TAGRISSO in 7% of patients and dosage interruptions of TAGRISSO in 35% of patients. Among the 46 patients who were rechallenged with TAGRISSO, 11% had recurrence of ILD/pneumonitis. In the 80 TAGRISSO-treated patients, ILD/pneumonitis resolved in 40%, resolved with sequelae in 1.3%, were resolving in 16%, did not resolve in 41%, and resulted in death in 1.3%.

For patients receiving TAGRISSO who have not received recent definitive platinum-based chemoradiation therapy, withhold TAGRISSO and promptly investigate for ILD in patients who present with worsening or respiratory symptoms which may be indicative of ILD (e.g., dyspnea, cough, and fever). Permanently discontinue TAGRISSO if ILD/pneumonitis is confirmed [see Dosage and Administration (2.5) and Adverse Reactions (6.1)].

For patients who have received recent definitive platinum-based chemoradiation therapy with Grade 1 ILD/pneumonitis continue TAGRISSO or interrupt and restart, as appropriate. Permanently discontinue TAGRISSO in patients diagnosed with Grade ≥2 ILD/pneumonitis [see Dosage and Administration (2.5) and Adverse Reactions (6.1)].

5.2 QTc Interval Prolongation

TAGRISSO can cause heart rate-corrected QT (QTc) interval prolongation. Of the 1813 patients treated with TAGRISSO monotherapy in clinical trials, 1.1% were found to have a QTc >500 msec, and 4.3% of patients had an increase from baseline QTc >60 msec [see Clinical Pharmacology (12.2)].

Of the 276 patients treated with TAGRISSO in combination with pemetrexed and platinum-based chemotherapy in the FLAURA2 study, 1.8% were found to have a QTc >500 msec, and 10.5% of patients had an increase from baseline QTc >60 msec.

No QTc-related arrhythmias were reported.

Clinical trials of TAGRISSO did not enroll patients with baseline QTc of >470 msec. Conduct periodic monitoring with ECGs and electrolytes in patients with congenital long QTc syndrome, congestive heart failure, electrolyte abnormalities, or those who are taking medications known to prolong the QTc interval. Permanently discontinue TAGRISSO in patients who develop QTc interval prolongation with signs/symptoms of life-threatening arrhythmia [see Dosage and Administration (2.5)].

5.3 Cardiomyopathy

TAGRISSO can cause cardiomyopathy, including cardiac failure, chronic cardiac failure, congestive heart failure, pulmonary edema or decreased ejection fraction.

Across clinical trials, cardiomyopathy occurred in 3.8% of the 1813 TAGRISSO-treated patients; 0.1% of cardiomyopathy cases were fatal.

In the FLAURA2 study, cardiomyopathy occurred in 9% of the 276 patients who received TAGRISSO in combination with pemetrexed and platinum-based chemotherapy; 1.1% of cardiomyopathy cases were fatal.

A decline in left ventricular ejection fraction (LVEF) ≥10 percentage points from baseline and to less than 50% LVEF occurred in 4.2% of 1557 patients who had baseline and at least one follow-up LVEF assessment. In the ADAURA study, 1.5% (5/325) of patients treated with TAGRISSO experienced LVEF decreases greater than or equal to 10 percentage points and a drop to less than 50%. In the LAURA study, following platinum-based chemoradiation therapy, 3% (4/135) of patients treated with TAGRISSO and no patients treated with placebo experienced LVEF decreases greater than or equal to 10 percentage points and a drop to less than 50%. In the FLAURA2 study, 8% (21/262) of patients treated with TAGRISSO in combination with pemetrexed and platinum-based chemotherapy, who had baseline and at least one follow-up LVEF assessment, experienced LVEF decreases greater than or equal to 10 percentage points and a drop to less than 50%.

For patients who will be receiving TAGRISSO monotherapy, conduct cardiac monitoring, including assessment of LVEF at baseline and during treatment, in patients with cardiac risk factors.

For patients who will be receiving TAGRISSO in combination with pemetrexed and platinum-based chemotherapy, conduct cardiac monitoring, including assessment of LVEF at baseline and during treatment, in all patients.

Assess LVEF in patients who develop relevant cardiac signs or symptoms during treatment. For symptomatic congestive heart failure, permanently discontinue TAGRISSO [see Dosage and Administration (2.5)].

5.4 Keratitis

Keratitis was reported in 0.6% of 1813 patients treated with TAGRISSO monotherapy in clinical trials. Promptly refer patients with signs and symptoms suggestive of keratitis (such as eye inflammation, lacrimation, light sensitivity, blurred vision, eye pain and/or red eye) to an ophthalmologist.

5.5 Erythema Multiforme Major, Stevens-Johnson Syndrome, and Toxic Epidermal Necrolysis

Postmarketing cases consistent with erythema multiforme major (EMM), Stevens-Johnson syndrome (SJS) and toxic epidermal necrolysis (TEN) have been reported in patients receiving TAGRISSO [see Postmarketing (6.2)]. Withhold TAGRISSO if EMM, SJS, or TEN is suspected and permanently discontinue if confirmed.

5.6 Cutaneous Vasculitis

Postmarketing cases of cutaneous vasculitis including leukocytoclastic vasculitis, urticarial vasculitis, and IgA vasculitis have been reported in patients receiving TAGRISSO [see Postmarketing (6.2)]. Withhold TAGRISSO if cutaneous vasculitis is suspected, evaluate for systemic involvement, and consider dermatology consultation. If no other etiology can be identified, consider permanent discontinuation of TAGRISSO based on severity.

5.7 Aplastic Anemia

Aplastic anemia has been reported in patients treated with TAGRISSO in clinical trials (0.06% of 1813) and postmarketing [see Postmarketing (6.2)]. Some cases had a fatal outcome. Inform patients of the signs and symptoms of aplastic anemia including but not limited to, new or persistent fevers, bruising, bleeding, and pallor. If aplastic anemia is suspected, withhold TAGRISSO and obtain a hematology consultation. If aplastic anemia is confirmed, permanently discontinue TAGRISSO [see Dosage and Administration (2.5)].

Perform complete blood count with differential before starting TAGRISSO, periodically throughout treatment, and more frequently if indicated.

5.8 Embryo-Fetal Toxicity

Based on data from animal studies and its mechanism of action, TAGRISSO can cause fetal harm when administered to a pregnant woman. In animal reproduction studies, osimertinib caused post-implantation fetal loss when administered during early development at a dose exposure 1.5 times the exposure at the recommended clinical dose. When males were treated prior to mating with untreated females, there was an increase in preimplantation embryonic loss at plasma exposures of approximately 0.5 times those observed at the recommended dose of 80 mg once daily. Verify pregnancy status of females of reproductive potential prior to initiating TAGRISSO. Advise pregnant women of the potential risk to a fetus. Advise females of reproductive potential to use effective contraception during treatment with TAGRISSO and for 6 weeks after the last dose. Advise males with female partners of reproductive potential to use effective contraception for 4 months after the last dose [see Use in Specific Populations (8.1and 8.3)].

6 ADVERSE REACTIONS

The following adverse reactions are discussed in greater detail in other sections of the labeling:

- Interstitial Lung Disease/Pneumonitis [see Error! Hyperlink reference not valid.]
- QTc Interval Prolongation [see Error! Hyperlink reference not valid.]
- Cardiomyopathy [see Error! Hyperlink reference not valid.]
- Keratitis [see Error! Hyperlink reference not valid.]
- Erythema multiforme, Stevens-Johnson syndrome, and Toxic epidermal necrolysis [see Error! Hyperlink reference not valid.]
- Cutaneous Vasculitis [see Error! Hyperlink reference not valid.]
- Aplastic Anemia [see Error! Hyperlink reference not valid.]

6.1 Clinical Trials Experience

Because clinical trials are conducted under widely varying conditions, adverse reaction rates observed in the clinical trials of a drug cannot be directly compared to rates in the clinical trials of another drug and may not reflect the rates observed in practice.

The data in the WARNINGS AND PRECAUTIONS section reflect exposure to TAGRISSO in 1813 patients with EGFR mutation-positive NSCLC who received TAGRISSO monotherapy at the recommended dose of 80 mg orally once daily until disease progression or unacceptable toxicity in four randomized, controlled trials [ADAURA (n=337), FLAURA (n=338), FLAURA2 (monotherapy arm; n=275), and AURA3 (n=279)] [see Clinical Studies (14)], two single arm trials [AURA Extension (n=201) {NCT01802632} and AURA2 (n=210)]{NCT02094261}, and one dose-finding study, AURA1 (n=173). Among 1813 patients who received TAGRISSO monotherapy, 82% were exposed for 6 months or longer and 67% were exposed for greater than one year. In this pooled safety population, the most common adverse reactions in ≥20% of 1813 patients who received TAGRISSO monotherapy were diarrhea (47%), rash (46%), musculoskeletal pain (38%), nail toxicity (34%), dry skin (32%), stomatitis (24%), and fatigue (21%). The most common laboratory abnormalities in ≥20% of 1813 patients who received TAGRISSO monotherapy were leukopenia (65%), lymphopenia (64%), thrombocytopenia (53%), anemia (52%), and neutropenia (36%). In addition to the 1813 patients, certain subsections in the WARNINGS AND PRECAUTIONS describe adverse reactions observed with exposure to TAGRISSO monotherapy (80 mg orally once daily until disease progression or unacceptable toxicity) following definitive platinum-based chemoradiation therapy (n=143) in the LAURA study.

The data described below reflect exposure to TAGRISSO (80 mg daily) in 337 patients with EGFR mutation-positive resectable NSCLC, 143 patients with EGFR mutation-positive locally advanced, unresectable (stage III) NSCLC, and 833 patients with EGFR mutation-positive locally advanced or metastatic NSCLC in five randomized, controlled trials [ADAURA (n=337), LAURA (n=143), FLAURA (n=279), FLAURA2 (monotherapy arm; n=275), and AURA3 (n=279)]. The data also reflect exposure to TAGRISSO at the recommended dose of 80 mg daily given in combination with pemetrexed and platinum-based chemotherapy in 276 patients with EGFR mutation-positive locally advanced or metastatic NSCLC in one randomized controlled trial [FLAURA2 (n=276)]. Patients with a history of interstitial lung disease, drug induced interstitial disease or radiation pneumonitis that required steroid treatment, serious arrhythmia or baseline QTc interval greater than 470 msec on electrocardiogram were excluded from enrollment in these studies.

Adjuvant Treatment of EGFR Mutation-Positive NSCLC - Monotherapy

The safety of TAGRISSO was evaluated in ADAURA, a randomized, double-blind, placebo-controlled trial for the adjuvant treatment of patients with EGFR exon 19 deletions or exon 21 L858R mutation-positive NSCLC who had complete tumor resection, with or without prior adjuvant chemotherapy. At time of DFS analysis, the median duration of exposure to TAGRISSO was 22.5 months.

Serious adverse reactions were reported in 16% of patients treated with TAGRISSO. The most common serious adverse reaction (≥1%) was pneumonia (1.5%). Adverse reactions leading to dose reductions occurred in 9% of patients treated with TAGRISSO. The most frequent adverse reactions leading to dose reductions or interruptions were diarrhea (4.5%), stomatitis (3.9%), nail toxicity (1.8%) and rash (1.8%). Adverse reactions leading to permanent discontinuation occurred in 11% of patients treated with TAGRISSO. The most frequent adverse reactions leading to discontinuation of TAGRISSO were interstitial lung disease (2.7%), and rash (1.2%).

Tables 4 and 5 summarize common adverse reactions and laboratory abnormalities which occurred in ADAURA.

Table 4. Adverse Reactions Occurring in ≥10% of Patients Receiving TAGRISSO in ADAURA [NCI CTCAE v4.0.]
Adverse Reaction | TAGRISSO (N=337) |  | PLACEBO (N=343)
Adverse Reaction | All Grades (%) | Grade 3 or higher [All events were grade 3.] (%) | All Grades (%) | Grade 3 or higher (%)
Gastrointestinal Disorders
Diarrhea [Includes diarrhea, colitis, enterocolitis, enteritis.] | 47 | 2.4 | 20 | 0.3
Stomatitis [Includes aphthous ulcer, cheilitis, gingival ulceration, glossitis, tongue ulceration, stomatitis and mouth ulceration.] | 32 | 1.8 | 7 | 0
Abdominal Pain [Includes abdominal discomfort, abdominal pain, abdominal lower pain, abdominal upper pain, epigastric discomfort, hepatic pain.] | 12 | 0.3 | 7 | 0
Skin Disorders
Rash [Includes rash, rash generalized, rash erythematous, rash macular, rash maculo-papular, rash papular, rash pustular, rash pruritic, rash vesicular, rash follicular, erythema, folliculitis, acne, dermatitis, dermatitis acneiform, dermatitis bullous, dermatitis exfoliative generalized, drug eruption, eczema, eczema asteatotic, lichen planus, skin erosion, pustule.] | 40 | 0.6 | 19 | 0
Nail toxicity [Includes nail bed disorder, nail bed inflammation, nail bed infection, nail discoloration, nail pigmentation, nail disorder, nail toxicity, nail dystrophy, nail infection, nail ridging, onychalgia, onychoclasis, onycholysis, onychomadesis, onychomalacia, paronychia.] | 37 | 0.9 | 3.8 | 0
Dry skin [Includes dry skin, skin fissures, xerosis, eczema, xeroderma.] | 29 | 0.3 | 7 | 0
Pruritus [Includes pruritus, pruritus generalized, eyelid pruritus.] | 19 | 0 | 9 | 0
Respiratory, Thoracic and Mediastinal Disorders
Cough [Includes cough, productive cough, upper-airway cough syndrome.] | 19 | 0 | 19 | 0
Musculoskeletal and Connective Tissue Disorders
Musculoskeletal Pain [Includes arthralgia, arthritis, back pain, bone pain, musculoskeletal chest pain, musculoskeletal pain, myalgia, neck pain, non-cardiac chest pain, pain in extremity, and spinal pain.] | 18 | 0.3 | 25 | 0.3
Infection and Infestation Disorders
Nasopharyngitis | 14 | 0 | 10 | 0
Upper respiratory tract infection | 13 | 0.6 | 10 | 0
Urinary Tract Infection [Includes cystitis, urinary tract infection, and urinary tract infection bacterial.] | 10 | 0.3 | 7 | 0
General Disorders and Administration Site Conditions
Fatigue [Includes asthenia, fatigue.] | 13 | 0.6 | 9 | 0.3
Metabolism and Nutrition Disorders
Decreased appetite | 13 | 0.6 | 3.8 | 0
Nervous System Disorders
Dizziness [Includes dizziness, vertigo, and vertigo positional.] | 10 | 0 | 9 | 0

Clinically relevant adverse reactions in ADAURA in <10% of patients receiving TAGRISSO were alopecia (6%), epistaxis (6%), interstitial lung disease (3%), palmar-plantar erythrodysesthesia syndrome (1.8%), skin hyperpigmentation (1.8%), urticaria (1.5%), keratitis (0.6%), QTc interval prolongation (0.6%), and erythema multiforme (0.3%). QTc interval prolongation represents the incidence of patients who had a QTcF prolongation >500 msec.

Table 5. Laboratory Abnormalities Worsening from Baseline in ≥20% of Patients in ADAURA
Laboratory Abnormality [NCI CTCAE v4.0] [Based on the number of patients with available follow-up laboratory data.] | TAGRISSO (N=337) |  | PLACEBO (N=343)
Laboratory Abnormality [NCI CTCAE v4.0] [Based on the number of patients with available follow-up laboratory data.] | All Grades (%) | Grade 3 or Grade 4 (%) | All Grades (%) | Grade 3 or Grade 4 (%)
Hematology
Leukopenia | 54 | 0 | 25 | 0
Thrombocytopenia | 47 | 0 | 7 | 0.3
Lymphopenia | 44 | 3.4 | 14 | 0.9
Anemia | 30 | 0 | 12 | 0.3
Neutropenia | 26 | 0.6 | 10 | 0.3
Chemistry
Hyperglycemia | 25 | 2.3 | 30 | 0.9
Hypermagnesemia | 24 | 1.3 | 14 | 1.5
Hyponatremia | 20 | 1.8 | 16 | 1.5

Laboratory abnormalities in ADAURA that occurred in <20% of patients receiving TAGRISSO was increased blood creatinine (10%).

Locally Advanced, Unresectable (Stage III) EGFR Mutation Positive NSCLC

The safety of TAGRISSO was evaluated in LAURA, a double blind, randomized (2:1), placebo controlled study conducted in 216 patients with EGFR exon 19 deletions or exon 21 L858R mutation positive, locally advanced, unresectable (stage III) NSCLC, who had not progressed during or following definitive platinum based chemoradiation therapy. Among patients who received TAGRISSO, 81% were exposed for 6 months or longer and 74% were exposed for one year or longer.

Serious adverse reactions were reported in 38% of patients treated with TAGRISSO. The most common serious adverse reactions (≥1%) included ILD/pneumonitis (13%), pneumonia (6%) and gastroenteritis (1.4%). Fatal adverse reactions occurred in 1.4% of patients who received TAGRISSO due to pneumonia (0.7%) and ILD/pneumonitis (0.7%).

Permanent discontinuation of TAGRISSO due to an adverse reaction occurred in 13% of patients. The adverse reactions resulting in permanent discontinuation of TAGRISSO in > 1 patient were ILD/pneumonitis (7%) and pneumonia (1.4%).

Dosage interruptions of TAGRISSO due to an adverse reaction occurred in 56% of patients. The adverse reactions requiring dosage interruption in ≥2% of patients were ILD/pneumonitis (35%), pneumonia (6%), COVID-19 (4.2%), neutropenia (2.1%), and QTc interval prolongation (2.1%).

Dose reductions of TAGRISSO due to an adverse reaction occurred in 8% of patients.

The most common adverse reactions, including laboratory abnormalities worsening from baseline, were lymphopenia, leukopenia, ILD/pneumonitis, thrombocytopenia, neutropenia, rash, diarrhea, nail toxicity, musculoskeletal pain, cough, and COVID-19.

Tables 6 and 7 summarize common adverse reactions and laboratory abnormalities which occurred in LAURA.

Table 6. Adverse Reactions in ≥10% of Patients Receiving TAGRISSO in LAURA [NCI CTCAE v5.0]
Adverse Reaction | TAGRISSO (N=143) |  | Placebo (N=73)
Adverse Reaction | Any Grade (%) | Grade 3 or 4(%) | Any Grade (%) | Grade 3 or 4 (%)
Respiratory, Thoracic and Mediastinal Disorders
ILD/pneumonitis [Includes radiation pneumonitis, radiation lung fibrosis, pneumonitis, interstitial lung disease (ILD), pulmonary fibrosis.] | 56 | 3.5 | 38 | 0
Cough [Includes cough, productive cough.] | 20 | 0 | 15 | 0
Skin Disorders
Rash [Includes rash, maculo-papular rash, pustular rash, pruritic rash, folliculitis, papule, dermatitis, acneiform dermatitis, atopic dermatitis, eczema, asteatotic eczema, acne, urticaria.] | 39 | 0.7 | 19 | 0
Nail toxicity [Includes nail bed disorder, nail disorder, nail discoloration, nail infection, onychoclasis, paronychia.] | 23 | 0 | 1.4 | 0
Dry skin [Includes dry skin, skin fissures, senile xerosis, xeroderma.] | 17 | 0.7 | 5 | 0
Pruritus | 13 | 0 | 7 | 0
Gastrointestinal Disorders
Diarrhea [Includes diarrhea, enteritis.] | 36 | 2.1 | 14 | 0
Stomatitis [Includes stomatitis, aphthous ulceration, mouth ulceration.] | 15 | 0 | 5 | 0
Musculoskeletal and Connective Tissue Disorders
Musculoskeletal pain [Includes musculoskeletal chest pain, myalgia, arthritis, arthralgia, back pain, bone pain, musculoskeletal pain, neck pain, pain in extremity, spinal osteoarthritis.] | 20 | 0.7 | 26 | 0
Infection and Infestation Disorders
COVID-19 [Includes COVID-19 and COVID-19 pneumonia.] | 20 | 0.7 | 10 | 0
Pneumonia [Includes pneumonia, aspiration pneumonia, viral pneumonia, Pneumocystis jiroveci pneumonia, Haemophilus pneumonia, lower respiratory tract infection.] | 15 | 3.5 | 10 | 5
Metabolism and Nutrition Disorders
Decreased appetite | 15 | 0.7 | 5 | 0

Clinically relevant adverse reactions in LAURA in <10% of patients receiving TAGRISSO were dyspnea (8%), urinary tract infection (8%), alopecia (1.4%), urticaria (1.4%), epistaxis (0.7%), keratitis (0.7%), and QTc interval prolongation (0.7%). QTc interval prolongation represents the incidence of patients who had a QTc prolongation >500 msec.

Table 7. Laboratory Abnormalities Worsening from Baseline in ≥20% of Patients in LAURA
Laboratory Abnormality [NCI CTCAE v5.0] [Each test incidence is based on the number of patients who had both baseline and at least one on-study laboratory measurement available (TAGRISSO arm: 142 and placebo arm: 72).] | TAGRISSO (N=143) |  | Placebo (N=73)
Laboratory Abnormality [NCI CTCAE v5.0] [Each test incidence is based on the number of patients who had both baseline and at least one on-study laboratory measurement available (TAGRISSO arm: 142 and placebo arm: 72).] | All Grades (%) | Grade 3 or 4 (%) | All Grades (%) | Grade 3 or 4 (%)
Hematology
Lymphopenia | 70 | 3.5 | 40 | 1.4
Leukopenia | 66 | 2.8 | 24 | 0
Thrombocytopenia | 51 | 1.4 | 8 | 1.4
Neutropenia | 42 | 2.1 | 15 | 1.4

A clinically relevant laboratory abnormality in LAURA that occurred in <20% of patients receiving TAGRISSO was increased blood creatinine (19%).

Previously Untreated EGFR Mutation-Positive Metastatic Non-Small Cell Lung Cancer - Monotherapy

The safety of TAGRISSO was evaluated in FLAURA, a multicenter international double-blind randomized (1:1) active‑controlled trial conducted in 556 patients with EGFR exon 19 deletion or exon 21 L858R mutation-positive, unresectable or metastatic NSCLC who had not received previous systemic treatment for advanced disease. The median duration of exposure to TAGRISSO was 16.2 months.

Serious adverse reactions were reported in 4% of patients treated with TAGRISSO; the most common serious adverse reactions (≥1%) were pneumonia (2.9%), ILD/pneumonitis (2.1%), and pulmonary embolism (1.8%). Dose reductions occurred in 2.9% of patients treated with TAGRISSO. The most frequent adverse reactions leading to dose reductions or interruptions were prolongation of the QT interval as assessed by ECG (4.3%), diarrhea (2.5%), and lymphopenia (1.1%). Adverse reactions leading to permanent discontinuation occurred in 13% of patients treated with TAGRISSO. The most frequent adverse reaction leading to discontinuation of TAGRISSO was ILD/pneumonitis (3.9%).

Tables 8 and 9 summarize common adverse reactions and laboratory abnormalities which occurred in FLAURA.

Table 8. Adverse Reactions Occurring in ≥10% of Patients Receiving TAGRISSO in FLAURA [NCI CTCAE v4.0]
Adverse Reaction | TAGRISSO; (N=279) |  | EGFR TKI comparator; (gefitinib or erlotinib); (N=277)
 | Any Grade; (%) | Grade 3 or higher (%) | Any Grade (%) | Grade 3 or higher (%)
Gastrointestinal Disorders
Diarrhea [One grade 5 (fatal) event was reported (diarrhea) for EGFR TKI comparator.] | 58 | 2.2 | 57 | 2.5
Stomatitis [Includes stomatitis and mouth ulceration.] | 32 | 0.7 | 22 | 1.1
Nausea | 14 | 0 | 19 | 0
Constipation | 15 | 0 | 13 | 0
Vomiting | 11 | 0 | 11 | 1.4
Skin Disorders
Rash [Includes rash, rash generalized, rash erythematous, rash macular, rash maculo-papular, rash papular, rash pustular, rash pruritic, rash vesicular, rash follicular, erythema, folliculitis, acne, dermatitis, dermatitis acneiform, drug eruption, skin erosion, pustule.] | 58 | 1.1 | 78 | 7
Dry skin [Includes dry skin, skin fissures, xerosis, eczema, xeroderma.] | 36 | 0.4 | 36 | 1.1
Nail toxicity [Includes nail bed disorder, nail bed inflammation, nail bed infection, nail discoloration, nail pigmentation, nail disorder, nail toxicity, nail dystrophy, nail infection, nail ridging, onychalgia, onychoclasis, onycholysis, onychomadesis, onychomalacia, paronychia.] | 35 | 0.4 | 33 | 0.7
Pruritus [Includes pruritus, pruritus generalized, eyelid pruritus.] | 17 | 0.4 | 17 | 0
General Disorders and Administration Site Conditions
Fatigue [Includes fatigue, asthenia.] | 21 | 1.4 | 15 | 1.4
Pyrexia | 10 | 0 | 4 | 0.4
Metabolism and Nutrition Disorders
Decreased appetite | 20 | 2.5 | 19 | 1.8
Respiratory, Thoracic and Mediastinal Disorders
Cough | 17 | 0 | 15 | 0.4
Dyspnea | 13 | 0.4 | 7 | 1.4
Neurologic Disorders
Headache | 12 | 0.4 | 7 | 0
Cardiac Disorders
Prolonged QT Interval [Includes prolonged QT interval reported as adverse reaction.] | 10 | 2.2 | 4 | 0.7
Infection and Infestation Disorders
Upper Respiratory Tract Infection | 10 | 0 | 7 | 0

Clinically relevant adverse reactions in FLAURA in <10% of patients receiving TAGRISSO were alopecia (7%), epistaxis (6%), interstitial lung disease (3.9%), urticaria (2.2%), palmar-plantar erythrodysesthesia syndrome (1.4%), QTc interval prolongation (1.1%), keratitis (0.4%), and skin hyperpigmentation (0.4%). QTc interval prolongation represents the incidence of patients who had a QTcF prolongation >500 msec.

Table 9. Laboratory Abnormalities Worsening from Baseline in ≥20% of Patients in FLAURA
Laboratory Abnormality [NCI CTCAE v4.0] [Each test incidence, except for hyperglycemia, is based on the number of patients who had both baseline and at least one on-study laboratory measurement available (TAGRISSO range: 267 - 273 and EGFR TKI comparator range: 256 - 268).] | TAGRISSO; (N=279) |  | EGFR TKI comparator; (gefitinib or erlotinib); (N=277)
Laboratory Abnormality [NCI CTCAE v4.0] [Each test incidence, except for hyperglycemia, is based on the number of patients who had both baseline and at least one on-study laboratory measurement available (TAGRISSO range: 267 - 273 and EGFR TKI comparator range: 256 - 268).] | All Grades; (%) | Grade 3 or; Grade 4; (%) | All Grades; (%) | Grade 3; or Grade 4; (%)
Hematology
Lymphopenia | 63 | 6 | 36 | 4.2
Anemia | 59 | 0.7 | 47 | 0.4
Thrombocytopenia | 51 | 0.7 | 12 | 0.4
Neutropenia | 41 | 3 | 10 | 0
Chemistry
Hyperglycemia [Hyperglycemia is based on the number of patients who had both baseline and at least one on-study laboratory measurement available: TAGRISSO (179) and EGFR comparator (191).] | 37 | 0 | 31 | 0.5
Hypermagnesemia | 30 | 0.7 | 11 | 0.4
Hyponatremia | 26 | 1.1 | 27 | 1.5
Increased AST | 22 | 1.1 | 43 | 4.1
Increased ALT | 21 | 0.7 | 52 | 8
Hypokalemia | 16 | 0.4 | 22 | 1.1
Hyperbilirubinemia | 14 | 0 | 29 | 1.1

A clinically relevant laboratory abnormality in FLAURA that occurred in <20% of patients receiving TAGRISSO was increased blood creatinine (9%).

Previously Untreated EGFR Mutation-Positive Locally Advanced or Metastatic Non-Small Cell Lung Cancer – TAGRISSO in Combination with Pemetrexed and Platinum-based Chemotherapy

The safety of TAGRISSO in combination with pemetrexed and platinum-based chemotherapy was evaluated in FLAURA2, a multicenter international open-label, randomized (1:1), active-controlled trial conducted in 557 patients with EGFR exon 19 deletion or exon 21 L858R mutation-positive, locally advanced or metastatic NSCLC who had not received previous systemic treatment for advanced disease. The median duration of exposure to TAGRISSO in combination with pemetrexed and platinum-based chemotherapy was 22.3 months and the median duration of exposure to TAGRISSO monotherapy was 19.3 months.

Serious adverse reactions were reported in 38% of patients treated with TAGRISSO in combination with pemetrexed and platinum-based chemotherapy; the most frequently reported serious adverse reactions (≥2%) in the combination arm were anemia (3.3%), COVID-19 (2.5%), pneumonia (2.5%), febrile neutropenia (2.2%), thrombocytopenia (2.2%), and pulmonary embolism (2.2%). Fatal adverse reactions occurred in 7% of patients who received TAGRISSO in combination with pemetrexed and platinum-based chemotherapy including pulmonary embolism (1.1%), pneumonia (1.1%) and cardiomyopathy (1.1%).

Dosage interruptions of TAGRISSO, when given with pemetrexed and platinum-based chemotherapy, due to an adverse reaction occurred in 44% of patients. Adverse reactions which required dosage interruption in ≥ 2% of patients included anemia (4.7%), neutropenia (4.3%), diarrhea (3.6%), febrile neutropenia (3.3%) and thrombocytopenia (2.9%).

Permanent discontinuation of TAGRISSO when given in combination with pemetrexed and platinum-based chemotherapy due to an adverse reaction occurred in 11% of patients. Adverse reactions which resulted in permanent discontinuation of TAGRISSO in ≥1% of patients included ILD/pneumonitis (2.9%), pneumonia (1.4%), and decreased ejection fraction (1.1%).

Adverse reactions leading to dose reduction of TAGRISSO occurred in 10% of patients treated with TAGRISSO in combination with pemetrexed and platinum-based chemotherapy. The most frequently reported adverse reactions leading to dose reduction of TAGRISSO in the combination arm in ≥1% of patients were diarrhea (1.1%) and rash (1.1%).

Tables 10 and 11 summarize common adverse reactions and laboratory abnormalities which occurred in FLAURA2.

Table 10. Adverse Reactions Occurring in ≥10% of Patients Receiving TAGRISSO in FLAURA2 [NCI CTCAE v5.0]
Adverse Reaction | TAGRISSO with Pemetrexed and Platinum-based Chemotherapy (N=276) |  | TAGRISSO (N=275)
Adverse Reaction | Any Grade (%) | Grade 3 or higher (%) | Any Grade (%) | Grade 3 or higher (%)
Skin Disorders
Rash [Includes rash, rash erythematous, rash macular, rash maculo-papular, rash papular, rash pustular, rash pruritic, rash vesicular, rash follicular, erythema, folliculitis, acne, dermatitis, dermatitis acneiform, drug eruption, skin erosion, pustule.] | 49 | 2.5 | 44 | 1.5
Nail toxicity [Includes nail bed disorder, nail bed inflammation, nail bed infection, nail discoloration, nail pigmentation, nail disorder, nail toxicity, nail dystrophy, nail infection, nail ridging, onychalgia, onychoclasis, onycholysis, onychomadesis, onychomalacia, paronychia.] | 27 | 0.7 | 32 | 0.4
Dry skin [Includes dry skin, skin fissures, xerosis, eczema, xeroderma.] | 24 | 0 | 31 | 0
Pruritus [Includes pruritus, eyelid pruritus.] | 8 | 0 | 11 | 0
Gastrointestinal Disorders
Diarrhea | 43 | 2.9 | 41 | 0.4
Stomatitis [Includes stomatitis and mouth ulceration.] | 31 | 0.4 | 21 | 0.4

Clinically relevant adverse reactions in FLAURA2 in <10% of patients receiving TAGRISSO in combination with pemetrexed and platinum-based chemotherapy were alopecia (9%), epistaxis (7%), palmar-plantar erythrodysesthesia syndrome (5%), interstitial lung disease (3.3%), skin hyperpigmentation (2.5%), QTc interval prolongation (1.8%), erythema multiforme (1.4%), urticaria (1.4%), and keratitis (0.7%). QTc interval prolongation represents the incidence of patients who had a QTcF prolongation >500 msec.

Table 11. Laboratory Abnormalities Worsening from Baseline in ≥20% of Patients in FLAURA2 [NCI CTCAE v5.0] [Findings based on test results presented as CTCAE grade shifts.]
Laboratory Abnormality [Each test incidence is based on the number of patients who had both baseline and at least one on-study laboratory measurement available (TAGRISSO with pemetrexed and platinum-based chemotherapy arm: 275 and TAGRISSO monotherapy arm: 275).] | TAGRISSO with Pemetrexed and Platinum-based Chemotherapy (N=276) |  | TAGRISSO (N=275)
Laboratory Abnormality [Each test incidence is based on the number of patients who had both baseline and at least one on-study laboratory measurement available (TAGRISSO with pemetrexed and platinum-based chemotherapy arm: 275 and TAGRISSO monotherapy arm: 275).] | All Grades (%) | Grade 3 or Grade 4 (%) | All Grades (%) | Grade 3 or Grade 4 (%)
Hematology
Leukopenia | 88 | 20 | 53 | 3.3
Thrombocytopenia | 85 | 16 | 44 | 1.8
Neutropenia | 85 | 36 | 40 | 4.7
Lymphopenia | 78 | 16 | 55 | 7
Chemistry
Blood creatinine increased | 22 | 0.4 | 8 | 0

Previously Treated EGFR T790M Mutation-Positive Metastatic Non-Small Cell Lung Cancer – Monotherapy

The safety of TAGRISSO was evaluated in AURA3, a multicenter international open label randomized (2:1) controlled trial conducted in 419 patients with unresectable or metastatic EGFR T790M mutation-positive NSCLC who had progressive disease following first line EGFR TKI treatment. A total of 279 patients received TAGRISSO 80 mg orally once daily until intolerance to therapy, disease progression, or investigator determination that the patient was no longer benefiting from treatment. A total of 136 patients received pemetrexed plus either carboplatin or cisplatin every three weeks for up to 6 cycles; patients without disease progression after 4 cycles of chemotherapy could continue maintenance pemetrexed until disease progression, unacceptable toxicity, or investigator determination that the patient was no longer benefiting from treatment. Left Ventricular Ejection Fraction (LVEF) was evaluated at screening and every 12 weeks. The median duration of treatment was 8.1 months for patients treated with TAGRISSO and 4.2 months for chemotherapy-treated patients. The trial population characteristics were: median age 62 years, age less than 65 (58%), female (64%), Asian (65%), never smokers (68%), and ECOG PS 0 or 1 (100%).

Serious adverse reactions were reported in 18% of patients treated with TAGRISSO and 26% in the chemotherapy group. No single serious adverse reaction was reported in 2% or more patients treated with TAGRISSO. One patient (0.4%) treated with TAGRISSO experienced a fatal adverse reaction (ILD/pneumonitis).

Dose reductions occurred in 2.9% of patients treated with TAGRISSO. The most frequent adverse reactions leading to dose reductions or interruptions were prolongation of the QT interval as assessed by ECG (1.8%), neutropenia (1.1%), and diarrhea (1.1%). Adverse reactions resulting in permanent discontinuation of TAGRISSO occurred in 7% of patients treated with TAGRISSO. The most frequent adverse reaction leading to discontinuation of TAGRISSO was ILD/pneumonitis (3%).

Tables 12 and 13 summarize common adverse reactions and laboratory abnormalities which occurred in TAGRISSO-treated patients in AURA3.

Table 12. Adverse Reactions Occurring in ≥10% of Patients Receiving TAGRISSO in AURA3 [NCI CTCAE v4.0.]
Adverse Reaction | TAGRISSO; (N=279) |  | Chemotherapy; (Pemetrexed/Cisplatin or; Pemetrexed/Carboplatin); (N=136)
Adverse Reaction | All Grades [No grade 4 events were reported.]; (%) | Grade 3/4; (%) | All Grades (%) | Grade 3/4; (%)
Gastrointestinal Disorders
Diarrhea | 41 | 1.1 | 11 | 1.5
Nausea | 16 | 0.7 | 49 | 3.7
Stomatitis [Includes stomatitis and mouth ulceration.] | 19 | 0 | 15 | 1.5
Constipation | 14 | 0 | 35 | 0
Vomiting | 11 | 0.4 | 20 | 2.2
Skin Disorders
Rash [Includes rash, rash generalized, rash erythematous, rash macular, rash maculo-papular, rash papular, rash pustular, erythema, folliculitis, acne, dermatitis, acneiform dermatitis, pustule.] | 34 | 0.7 | 6 | 0
Dry skin [Includes dry skin, eczema, skin fissures, xerosis.] | 23 | 0 | 4.4 | 0
Nail toxicity [Includes nail disorders, nail bed disorders, nail bed inflammation, nail bed tenderness, nail discoloration, nail disorder, nail dystrophy, nail infection, nail ridging, nail toxicity, onychalgia, onychoclasis, onycholysis, onychomadesis, paronychia.] | 22 | 0 | 1.5 | 0
Pruritus [Includes pruritus, pruritus generalized, eyelid pruritus.] | 13 | 0 | 5 | 0
General Disorders and Administration Site Conditions
Fatigue [Includes fatigue, asthenia.] | 22 | 1.8 | 40 | 5.1
Metabolism and Nutrition Disorders
Decreased appetite | 18 | 1.1 | 36 | 2.9
Respiratory, Thoracic and Mediastinal Disorders
Cough | 17 | 0 | 14 | 0
Musculoskeletal and Connective Tissue Disorders
Back pain | 10 | 0.4 | 9 | 0.7

Clinically relevant adverse reactions in AURA3 in <10% of patients receiving TAGRISSO were epistaxis (5%), interstitial lung disease (3.9%), alopecia (3.6%), urticaria (2.9%), palmar-plantar erythrodysesthesia syndrome (1.8%), QTc interval prolongation (1.4%), keratitis (1.1%), and erythema multiforme (0.7%), and skin hyperpigmentation (0.4%). QTc interval prolongation represents the incidence of patients who had a QTcF prolongation >500 msec.

Table 13. Laboratory Abnormalities Worsening from Baseline in ≥20% of Patients in AURA3
Laboratory Abnormality [NCI CTCAE v4.0] [Each test incidence, except for hyperglycemia, is based on the number of patients who had both baseline and at least one on-study laboratory measurement available (TAGRISSO 279, Chemotherapy comparator 131).] | TAGRISSO; (N=279) |  | Chemotherapy (Pemetrexed/Cisplatin or Pemetrexed/Carboplatin); (N=131)
Laboratory Abnormality [NCI CTCAE v4.0] [Each test incidence, except for hyperglycemia, is based on the number of patients who had both baseline and at least one on-study laboratory measurement available (TAGRISSO 279, Chemotherapy comparator 131).] | All Grades; (%) | Grade 3 or Grade 4; (%) | All Grades; (%) | Grade 3 or Grade 4; (%)
Hematology
Anemia | 43 | 0 | 79 | 3.1
Lymphopenia | 63 | 8 | 61 | 10
Thrombocytopenia | 46 | 0.7 | 48 | 7
Neutropenia | 27 | 2.2 | 49 | 12
Chemistry
Hypermagnesemia | 27 | 1.8 | 9 | 1.5
Hyponatremia | 26 | 2.2 | 36 | 1.5
Hyperglycemia [Hyperglycemia is based on the number of patients who had both baseline and at least one on-study laboratory measurement available (TAGRISSO 270, Chemotherapy 5; fasting glucose was not a protocol requirement for patients in the chemotherapy arm).] | 20 | 0 | NA | NA
Hypokalemia | 9 | 1.4 | 18 | 1.5
NA=Not Applicable

Clinically relevant laboratory abnormalities in AURA3 that occurred in <20% of patients receiving TAGRISSO included increased blood creatinine (7%).

Other Clinical Trials Experience

The following adverse reaction has been reported following administration of TAGRISSO: increased blood creatine phosphokinase.

6.2 Postmarketing Experience

The following adverse reactions have been identified during post-approval use of TAGRISSO. Because these reactions are reported voluntarily from a population of uncertain size, it is not always possible to reliably estimate their frequency or establish a causal relationship to drug exposure.

  - Skin and subcutaneous tissue: Erythema multiforme major (EMM), Stevens-Johnson syndrome (SJS), toxic epidermal necrolysis (TEN), cutaneous vasculitis, erythema dyschromicum perstans
  - Blood and lymphatic system disorders: Aplastic anemia

7 DRUG INTERACTIONS

7.1 Effect of Other Drugs on Osimertinib

Strong CYP3A Inducers

Co-administering TAGRISSO with a strong CYP3A4 inducer decreased the exposure of osimertinib compared to administering TAGRISSO alone [see Clinical Pharmacology (12.3)]. Decreased osimertinib exposure may lead to reduced efficacy.

Avoid co-administering TAGRISSO with strong CYP3A inducers. Increase the TAGRISSO dosage when co-administering with a strong CYP3A4 inducer if concurrent use is unavoidable [see Dosage and Administration (2.5)]. No dose adjustments are required when TAGRISSO is used with moderate and/or weak CYP3A inducers.

7.2 Effect of Osimertinib on Other Drugs

Co-administering TAGRISSO with a breast cancer resistant protein (BCRP) or P-glycoprotein (P-gp) substrate increased the exposure of the substrate compared to administering it alone [see Clinical Pharmacology (12.3)]. Increased BCRP or P-gp substrate exposure may increase the risk of exposure-related toxicity.

Monitor for adverse reactions of the BCRP or P-gp substrate, unless otherwise instructed in its approved labeling, when co-administered with TAGRISSO.

7.3 Drugs That Prolong the QTc Interval

The effect of co-administering medicinal products known to prolong the QTc interval with TAGRISSO is unknown. When feasible, avoid concomitant administration of drugs known to prolong the QTc interval with known risk of Torsades de pointes. If not feasible to avoid concomitant administration of such drugs, conduct periodic ECG monitoring [see Error! Hyperlink reference not valid. and Clinical Pharmacology (12.2)].

8 USE IN SPECIFIC POPULATIONS

8.1 Pregnancy

Risk Summary

Based on data from animal studies and its mechanism of action [see Clinical Pharmacology (12.1)], TAGRISSO can cause fetal harm when administered to a pregnant woman. There are no available data on TAGRISSO use in pregnant women. Administration of osimertinib to pregnant rats was associated with embryolethality and reduced fetal growth at plasma exposures 1.5 times the exposure at the recommended clinical dose (see Data). Advise pregnant women of the potential risk to a fetus.

In the U.S. general population, the estimated background risk of major birth defects and miscarriage in clinically recognized pregnancies is 2% to 4% and 15% to 20%, respectively.

Data

Animal Data

When administered to pregnant rats prior to embryonic implantation through the end of organogenesis (gestation days 2-20) at a dose of 20 mg/kg/day, which produced plasma exposures of approximately 1.5 times the clinical exposure, osimertinib caused post-implantation loss and early embryonic death. When administered to pregnant rats from implantation through the closure of the hard palate (gestation days 6 to 16) at doses of 1 mg/kg/day and above (0.1 times the AUC observed at the recommended clinical dose of 80 mg once daily), an equivocal increase in the rate of fetal malformations and variations was observed in treated litters relative to those of concurrent controls. When administered to pregnant dams at doses of 30 mg/kg/day during organogenesis through lactation Day 6, osimertinib caused an increase in total litter loss and postnatal death. At a dose of 20 mg/kg/day, osimertinib administration during the same period resulted in increased postnatal death as well as a slight reduction in mean pup weight at birth that increased in magnitude between lactation days 4 and 6.

8.2 Lactation

Risk Summary

There are no data on the presence of osimertinib or its active metabolites in human milk, the effects of osimertinib on the breastfed infant or on milk production. Administration to rats during gestation and early lactation was associated with adverse effects, including reduced growth rates and neonatal death [see Use in Specific Populations (8.1)]. Because of the potential for serious adverse reactions in breastfed infants from osimertinib, advise women not to breastfeed during treatment with TAGRISSO and for 2 weeks after the last dose.

8.3 Females and Males of Reproductive Potential

Based on animal data, TAGRISSO can cause malformations, embryo lethality, and postnatal death at doses resulting in exposures 1.5 times or less the human exposure at the clinical dose of 80 mg daily [see Use in Specific Populations (8.1)].

Pregnancy Testing

Verify the pregnancy status of females of reproductive potential prior to initiating TAGRISSO.

Contraception

Females

Advise females of reproductive potential to use effective contraception during treatment with TAGRISSO and for 6 weeks after the last dose [see Use in Specific Populations (8.1)].

Males

Advise male patients with female partners of reproductive potential to use effective contraception during and for 4 months following the last dose of TAGRISSO [see Nonclinical Toxicology (13.1)].

Infertility

Based on animal studies, TAGRISSO may impair fertility in females and males of reproductive potential. The effects on female fertility showed a trend toward reversibility. It is not known whether the effects on male fertility are reversible [see Nonclinical Toxicology (13.1)].

8.4 Pediatric Use

The safety and effectiveness of TAGRISSO in pediatric patients have not been established.

8.5 Geriatric Use

Monotherapy

Of the 1813 patients with EGFR exon 19 deletion or exon 21 L858R mutation-positive NSCLC who were treated with TAGRISSO monotherapy, 770 patients were ≥65 years and 207 patients were ≥75 years of age [see Adverse Reactions (6.1)]. Exploratory analysis suggests a higher incidence of Grade 3 or higher adverse reactions (43% vs 33%) and more frequent dosage modifications for adverse reactions (34% vs 23%) in patients 65 years or older as compared to those younger than 65 years. No overall differences in safety or effectiveness were observed between patients 65 years or older and younger patients.

TAGRISSO Following Definitive Platinum-based Chemoradiation Therapy

Of the 142 patients with EGFR exon 19 deletion or exon 21 L858R mutation-positive, locally advanced unresectable (Stage III) NSCLC treated with TAGRISSO following definitive platinum-based chemoradiation therapy, 62 patients were ≥65 years and 13 patients were ≥75 years of age [see Adverse Reactions (6.1)]. No overall differences in safety or effectiveness were observed between patients 65 years or older and younger patients.

TAGRISSO in Combination with Pemetrexed and Platinum-based Chemotherapy

Of the 276 patients with EGFR exon 19 deletion or exon 21 L858R mutation-positive, locally advanced or metastatic NSCLC treated with TAGRISSO in combination with pemetrexed and platinum-based chemotherapy, 104 patients were ≥65 years and 23 patients were ≥75 years of age [see Adverse Reactions (6.1)]. Exploratory analysis suggests a higher incidence of Grade 3 or higher adverse reactions (68% vs 61%) and more frequent dosage modifications for adverse reactions (55% vs 43%) in patients 65 years or older as compared to those younger than 65 years. Clinical studies of TAGRISSO in combination with pemetrexed and platinum-based chemotherapy did not include sufficient numbers of patients age 65 and over to determine whether they respond differently from younger patients.

8.6 Renal Impairment

No dose adjustment is recommended in patients with creatinine clearance (CLcr) 15 - 89 mL/min, as estimated by Cockcroft-Gault. There is no recommended dose of TAGRISSO for patients with end-stage renal disease (CLcr <15 mL/min) [see Clinical Pharmacology (12.3)].

8.7 Hepatic Impairment

No dose adjustment is recommended in patients with mild to moderate hepatic impairment (Child-Pugh A and B or total bilirubin ≤ ULN and AST > ULN or total bilirubin 1 to 3 times ULN and any AST). There is no recommended dose for TAGRISSO for patients with severe hepatic impairment (total bilirubin between 3 to 10 times ULN and any AST) [see Clinical Pharmacology (12.3)].

11 DESCRIPTION

Osimertinib is a kinase inhibitor for oral use. The molecular formula for osimertinib mesylate is C28H33N7O2•CH4O3S, and the molecular weight is 596 g/mol. The chemical name is N-(2-{2-dimethylaminoethyl-methylamino}-4-methoxy-5-{[4-(1-methylindol-3-yl)pyrimidin-2-yl]amino}phenyl)prop-2-enamide mesylate salt. Osimertinib has the following structural formula (as osimertinib mesylate):

TAGRISSO tablets contain 40 or 80 mg of osimertinib, equivalent to 47.7 and 95.4 mg of osimertinib mesylate, respectively. Inactive ingredients in the tablet core are mannitol, microcrystalline cellulose, low-substituted hydroxypropyl cellulose and sodium stearyl fumarate. The tablet coating consists of polyvinyl alcohol, titanium dioxide, macrogol 3350, talc, ferric oxide yellow, ferric oxide red and ferric oxide black.

12 CLINICAL PHARMACOLOGY

12.1 Mechanism of Action

Osimertinib is a kinase inhibitor of the epidermal growth factor receptor (EGFR), which binds irreversibly to certain mutant forms of EGFR (T790M, L858R, and exon 19 deletions) at approximately 9-fold lower concentrations than wild-type. Two pharmacologically-active metabolites (AZ7550 and AZ5104 circulating at approximately 10% of the parent) with similar inhibitory profiles to osimertinib have been identified in the plasma after oral administration of osimertinib. AZ7550 showed a similar potency to osimertinib, while AZ5104 showed greater potency against exon 19 deletion and T790M mutants (approximately 8-fold) and wild-type (approximately 15-fold) EGFR. In vitro, osimertinib also inhibited the activity of HER2, HER3, HER4, ACK1, and BLK at clinically relevant concentrations.

In cultured cells and animal tumor implantation models, osimertinib exhibited anti-tumor activity against NSCLC lines harboring EGFR-mutations (T790M/L858R, L858R, T790M/exon 19 deletion, and exon 19 deletion) and, to a lesser extent, wild-type EGFR amplifications. Osimertinib distributed to the brain in multiple animal species (monkey, rat, and mouse) with brain to plasma AUC ratios of approximately 2 following oral dosing. These data are consistent with observations of tumor regression and increased survival in osimertinib- versus control-treated animals in a pre-clinical mutant-EGFR intracranial mouse metastasis xenograft model (PC9; exon 19 deletion).

12.2 Pharmacodynamics

Based on an analysis of dose-exposure response relationships over the dose range of 20 mg (0.25 times the recommended dose) to 240 mg (3 times the recommended dose), no apparent relationship between osimertinib exposure and overall response rate, duration of response and progression-free survival was identified; however, there were limited data available at the 20 mg dose. Over the same dose range, increased exposure led to increased probability of adverse reactions, specifically rash, diarrhea and ILD.

Cardiac Electrophysiology

The QTc interval prolongation potential of osimertinib was assessed in 210 patients who received TAGRISSO 80 mg daily in AURA2. A central tendency analysis of the QTcF data at steady-state demonstrated that the maximum mean change from baseline was 16.2 msec (upper bound of two-sided 90% confidence interval (CI) 17.6 msec). A pharmacokinetic/pharmacodynamic analysis in AURA2 suggested a concentration-dependent QTc interval prolongation of 14 msec (upper bound of two-sided 90% CI: 16 msec) at a dose of TAGRISSO 80 mg.

12.3 Pharmacokinetics

The area under the plasma concentration-time curve (AUC) and maximal plasma concentration (Cmax) of osimertinib increased dose proportionally over 20 to 240 mg dose range (i.e., 0.25 to 3 times the recommended dosage) after oral administration and exhibited linear pharmacokinetics (PK). Administration of TAGRISSO orally once daily resulted in approximately 3-fold accumulation with steady-state exposures achieved after 15 days of dosing. At steady state, the Cmax to Cmin (minimal concentration) ratio was 1.6-fold.

The pharmacokinetics in patients treated with osimertinib in combination with pemetrexed and platinum-based chemotherapy are similar to those in patients treated with osimertinib monotherapy.

Absorption

The median time to Cmax of osimertinib was 6 hours (range 3-24 hours).

Following administration of a 20 mg TAGRISSO tablet with a high-fat, high-calorie meal (containing approximately 58 grams of fat and 1000 calories), the Cmax and AUC of osimertinib were comparable to that under fasting conditions.

Distribution

The mean volume of distribution at steady-state (Vss/F) of osimertinib was 918 L. Plasma protein binding of osimertinib was 95%. PET brain imaging studies in healthy volunteers and in patients with brain metastases show that osimertinib is distributed to the brain following intravenous injection of a micro dose of ^11C-labeled osimertinib.

Elimination

Osimertinib plasma concentrations decreased with time and a population estimated mean half-life of osimertinib was 48 hours, and oral clearance (CL/F) was 14.3 (L/h).

Metabolism

The main metabolic pathways of osimertinib were oxidation (predominantly CYP3A) and dealkylation in vitro. Two pharmacologically active metabolites (AZ7550 and AZ5104) have been identified in the plasma after TAGRISSO oral administration. The geometric mean exposure (AUC) of each metabolite (AZ5104 and AZ7550) was approximately 10% of the exposure of osimertinib at steady-state.

Excretion

Osimertinib is primarily eliminated in the feces (68%) and to a lesser extent in the urine (14%). Unchanged osimertinib accounted for approximately 2% of the elimination.

Specific Populations

No clinically significant differences in the pharmacokinetics of osimertinib were observed based on age, sex, ethnicity, body weight, baseline albumin, line of therapy, smoking status, renal function (creatinine clearance (CLcr) ≥15 mL/min by Cockcroft-Gault), or hepatic impairment (Child-Pugh A and B, or total bilirubin ≤ ULN and AST > ULN or total bilirubin between 1 to 3 times ULN and any AST). The pharmacokinetics of osimertinib in patients with end-stage renal disease (CLcr <15 mL/min) or severe hepatic impairment (total bilirubin 3 to 10 times ULN and any AST) are unknown [see Use in Specific Populations (8.6) and (8.7)].

Drug Interaction Studies

Effect of Other Drugs on TAGRISSO in Clinical Pharmacokinetic Studies Strong CYP3A Inducers: The steady-state AUC of osimertinib was reduced by 78% in patients when co-administered with rifampin (600 mg daily for 21 days) [see Drug Interactions (7.1)].

Strong CYP3A Inhibitors: Co-administering TAGRISSO with 200 mg itraconazole twice daily (a strong CYP3A4 inhibitor) had no clinically significant effect on the exposure of osimertinib (AUC increased by 24% and Cmax decreased by 20%).

Gastric Acid Reducing Agents: The exposure of osimertinib was not affected by concurrent administration of a single 80 mg TAGRISSO tablet following 40 mg omeprazole administration for 5 days.

Effect of Osimertinib on Other Drugs in Clinical Pharmacokinetic Studies

BCRP substrates: Co-administering TAGRISSO with rosuvastatin (a BCRP substrate) increased rosuvastatin AUC by 35% and Cmax by 72% [see Drug Interactions (7.2)].

P-gp substrates: Co-administering TAGRISSO with fexofenadine (a P-gp substrate) increased fexofenadine AUC and Cmax by 56% and 76% after a single dose and 27% and 25% at steady state, respectively.

CYP3A4 substrates: Co-administering TAGRISSO with simvastatin (a CYP3A4 substrate) had no clinically significant effect on the exposure of simvastatin.

In Vitro Studies

CYP450 Metabolic Pathways: Osimertinib does not inhibit CYP1A2, 2A6, 2B6, 2C8, 2C9, 2C19, 2D6 and 2E1. Osimertinib induced CYP1A2 enzymes.

Transporter Systems: Osimertinib is a substrate of P-glycoprotein and BCRP and is not a substrate of OATP1B1 and OATP1B3. Osimertinib is an inhibitor of BCRP and does not inhibit OAT1, OAT3, OATP1B1, OATP1B3, MATE1, MATE2K and OCT2.

13 NONCLINICAL TOXICOLOGY

13.1 Carcinogenesis, Mutagenesis, Impairment of Fertility

A 2-year carcinogenicity was conducted in male and female rats at oral osimertinib doses of 1, 3, and 10 mg/kg/day. Osimertinib increased the incidences of hemangioma and combined hemangioma/hemangiosarcoma in the mesenteric lymph node and whole body at 10 mg/kg/day (0.2 times the human exposure based on AUC at the clinical dose of 80 mg once daily). Administration of osimertinib to male and female rasH2 transgenic mice by oral gavage daily for 26 weeks did not result in an increased incidence of neoplasms at doses up to 10 mg/kg/day.

Osimertinib did not induce mutations in the bacterial reverse mutation (Ames) assay and was not genotoxic in mouse lymphoma cells or in the rat in vivo micronucleus assay.

Based on studies in animals, male fertility may be impaired by treatment with TAGRISSO. Degenerative changes were present in the testes in rats and dogs exposed to osimertinib for 1 month or more with evidence of reversibility in the rat. Following administration of osimertinib to rats for approximately 10 weeks at a dose of 40 mg/kg, at exposures 0.5 times the AUC observed at the recommended clinical dose of 80 mg once daily, there was a reduction in male fertility, demonstrated by increased pre-implantation loss in untreated females mated to treated males.

Based on studies in animals, female fertility may be impaired by treatment with TAGRISSO. In repeat dose toxicity studies, histological evidence of anestrus, corpora lutea degeneration in the ovaries and epithelial thinning in the uterus and vagina were seen in rats exposed to osimertinib for 1 month or more at exposures 0.3 times the AUC observed at the recommended clinical dose of 80 mg once daily. Findings in the ovaries seen following 1 month of dosing exhibited evidence of reversibility. In a female fertility study in rats, administration of osimertinib from 2 weeks prior to mating through Day 8 of gestation at a dose of 20 mg/kg/day (approximately 1.5 times the Cmax at the recommended dose of 80 mg once daily) had no effects on estrous cycling or the number of females becoming pregnant, but caused early embryonic deaths. These findings showed evidence of reversibility when females were mated 1 month after treatment discontinuation.

13.2 Animal Toxicology and/or Pharmacology

Administration of osimertinib resulted in histological findings of lens fiber degeneration in the 2-year rat carcinogenicity study at ≥3 mg/kg/day (exposures 0.2 times the human exposure based on AUC). These findings were consistent with the ophthalmoscopic observation of lens opacities, which were first noted from week 52 and showed a gradual increase in incidence and severity with increased duration of dosing.

14 CLINICAL STUDIES

14.1 Adjuvant Treatment of Early-Stage EGFR Mutation-Positive Non-Small Cell Lung Cancer (NSCLC)

The efficacy of TAGRISSO was demonstrated in a randomized, double-blind, placebo-controlled trial (ADAURA [NCT02511106]) for the adjuvant treatment of patients with EGFR exon 19 deletions or exon 21 L858R mutation-positive NSCLC who had complete tumor resection, with or without prior adjuvant chemotherapy. Eligible patients with resectable tumors (stage IB – IIIA according to American Joint Commission on Cancer [AJCC] 7th edition) were required to have predominantly non-squamous histology and EGFR exon 19 deletions or exon 21 L858R mutations identified prospectively from tumor tissue in a central laboratory by the cobas® EGFR Mutation Test. Patients with clinically significant uncontrolled cardiac disease, prior history of ILD/pneumonitis, or who received treatment with any EGFR kinase inhibitor were not eligible for the study.

Patients were randomized (1:1) to receive TAGRISSO 80 mg orally once daily or placebo following recovery from surgery and standard adjuvant chemotherapy if given. Patients who did not receive adjuvant chemotherapy were randomized within 10 weeks and patients who received adjuvant chemotherapy were randomized within 26 weeks following surgery. Randomization was stratified by mutation type (exon 19 deletions or exon 21 L858R mutations), race (Asian or non-Asian) and pTNM staging (IB or II or IIIA) according to AJCC 7th edition. Treatment was given for 3 years or until disease recurrence, or unacceptable toxicity.

The major efficacy outcome measure was disease-free survival (DFS, defined as reduction in the risk of disease recurrence or death) in patients with stage II – IIIA NSCLC determined by investigator assessment. Additional efficacy outcome measures included DFS in the overall population (patients with stage IB – IIIA NSCLC), and overall survival (OS) in patients with stage II – IIIA NSCLC and in the overall population.

A total of 682 patients were randomized to TAGRISSO (n=339) or placebo (n=343). The median age was 63 years (range 30-86 years); 70% were female; 64% were Asian and 72% were never smokers. Baseline World Health Organization (WHO) performance status was 0 (64%) or 1 (36%); 31% had stage IB, 35% II, and 34% IIIA. With regard to EGFR mutation status, 55% were exon 19 deletions and 45% were exon 21 L858R mutations. The majority (60%) of patients received adjuvant chemotherapy prior to randomization (27% IB; 70% II, 79% IIIA).

ADAURA demonstrated a statistically significant difference in DFS for patients treated with TAGRISSO compared to patients treated with placebo. The final analysis of OS demonstrated a statistically significant improvement in OS for patients treated with TAGRISSO compared to patients treated with placebo. Median OS was not reached in either arm. In the overall population (IB-IIIA), the median follow-up time was 61.5 months in both treatment arms. Efficacy results from ADAURA are summarized in Table 14 and Figures 1 and 2, respectively.

Table 14. Efficacy Results in ADAURA according to Investigator Assessment
 | STAGE II-IIIA POPULATION |  | STAGE IB-IIIA POPULATION
Efficacy Parameter | TAGRISSO (N=233) | PLACEBO (N=237) | TAGRISSO (N=339) | PLACEBO (N=343)
Disease-Free Survival (DFS)
DFS events (%) | 26 (11) | 130 (55) | 37 (11) | 159 (46)
Recurrent disease (%) | 26 (11) | 129 (54) | 37 (11) | 157 (46)
Deaths (%) | 0 | 1 (0.4) | 0 | 2 (0.6)
Median DFS, months (95% CI) | NR (38.8, NE) | 19.6 (16.6, 24.5) | NR (NE, NE) | 27.5 (22.0, 35.0)
Hazard ratio (95% CI) [Stratified by race (Asian vs other races), mutation status (Ex19del vs L858R), and pTNM staging.] [Pike estimator.] | 0.17 (0.12, 0.23) |  | 0.20 (0.15, 0.27)
p-value [Stratified log-rank test.] | <0.0001 |  | <0.0001
Overall Survival (OS)
Number of deaths (%) | 35 (15) | 65 (27) | 42 (12) | 82 (24)
Hazard Ratio (95% CI) | 0.49 (0.33, 0.73) |  | 0.49 (0.34, 0.70)
p-value | 0.0004 |  | <0.0001
DFS results based on investigator assessment.
CI=Confidence Interval; NE=Not Estimable; NR=Not Reached

Figure 1. Kaplan-Meier Curves of Disease-Free Survival (Overall Population) by Investigator Assessment in ADAURA

Figure 2. Kaplan-Meier Curves of Overall Survival (Overall Population) in ADAURA

In an exploratory analysis of site(s) of relapse, the proportion of patients with CNS involvement at the time of disease recurrence was 5 patients (1.5%) on the TAGRISSO arm and 34 patients (10%) on the placebo arm.

14.2 Locally Advanced, Unresectable (Stage III) EGFR Mutation Positive NSCLC

The efficacy of TAGRISSO was evaluated in the LAURA trial [NCT03521154], a double blind, randomized, placebo-controlled study in adult patients with locally advanced, unresectable stage III NSCLC with EGFR exon 19 deletions or exon 21 L858R mutations whose disease had not progressed during or following definitive platinum-based chemoradiation therapy. Eligible patients were randomized within 42 days prior to study randomization and had a WHO performance status of 0 or 1. Prior to study enrollment, patients received concurrent chemoradiation therapy (cCRT) or sequential chemoradiation therapy (sCRT) regimens, where at least 2 cycles every 3 weeks or 5 doses of weekly platinum-based chemotherapy and definitive radiation were to be completed ≤6 weeks prior to randomization. The study excluded patients who had progressive disease during or following definitive chemoradiation therapy and patients with Grade ≥2 pneumonitis after chemoradiation therapy or any ILD prior to chemoradiation therapy. Patient tumor tissue samples were required to have an EGFR exon 19 deletion or exon 21 L858R mutation, as identified by the cobas® EGFR Mutation Test v2 in a central laboratory or by an FDA-approved test at a CLIA certified or accredited laboratory.

Patients were randomized (2:1) to receive either TAGRISSO 80 mg orally once daily or placebo until disease progression or unacceptable toxicity. Randomization was stratified by prior chemoradiation strategy (cCRT vs sCRT), tumor staging prior to chemoradiation (IIIA vs IIIB/IIIC), and by region (China versus rest of the world). Post progression, all patients were offered open label TAGRISSO if, in the opinion of the treating healthcare provider, there was an expected clinical benefit. Tumor assessments were performed every 8 weeks until week 48, and then every 12 weeks.

The major efficacy outcome measure was progression free survival (PFS) as assessed by blinded independent central review (BICR). Additional efficacy outcome measures included OS and CNS PFS.

A total of 216 patients were randomized (2:1) to TAGRISSO (n=143) or placebo (n=73). The study population characteristics were: median age 63 years (range 36-84 years); 13% ≥75 years old; 61% female; 82% Asian, 14% White, 1.4% American Indian or Alaska Native and 2.3% had reported race as other; 6% were Hispanic or Latino; and 70% were never smokers. Baseline WHO performance status was 0 (51%) or 1 (49%); 35% of patients had stage IIIA, 49% of patients had stage IIIB and 16% of patients had stage IIIC NSCLC; 4% had squamous and 96% had non-squamous histology; 54% had exon 19 deletions and 45% had exon 21 L858R mutations. Prior to randomization, 89% of patients received cCRT and 11% of patients received sCRT. All patients received platinum-based chemotherapy (55% carboplatin-based chemotherapy and 44% cisplatin-based chemotherapy). The median total dose of radiation was 60 Gy for patients in both arms.

LAURA demonstrated a statistically significant improvement in PFS for patients randomized to TAGRISSO as compared to placebo. Efficacy results from LAURA are summarized in Table 15, and the Kaplan-Meier curve for PFS is shown in Figure 3. While OS results were immature at the current analysis, with 36% of pre-specified deaths for the final analysis reported, no trend towards a detriment was observed.

Table 15. Efficacy Results in LAURA
Efficacy Parameter | TAGRISSO (N=143) | Placebo (N=73)
Progression-Free Survival
PFS events (%) | 57 (40) | 63 (86)
Progressive disease (%) | 53 (37) | 62 (85)
Death [Without documented radiological disease progression.] (%) | 4 (3) | 1 (1)
Median PFS in months (95% CI) | 39.1 (31.5, NE) | 5.6 (3.7, 7.4)
Hazard Ratio (95% CI) [Stratified by disease stage prior to chemotherapy (IIIA vs IIIB/IIIC).] [Pike estimator.] | 0.16 (0.10, 0.24)
p-value [Stratified log-rank test.] | <0.001
Overall Response Rate [Confirmed responses.]
ORR, % (95% CI) | 54 (45, 62) | 26 (17, 38)
CI=Confidence Interval, NE=Not Estimable
PFS and ORR results as assessed by BICR.

Figure 3. Kaplan-Meier Curves of PFS as assessed by BICR in LAURA

All patients underwent magnetic resonance imaging (MRI) brain scans at baseline and at each follow-up during the study. In an exploratory analysis of site(s) of relapse, the proportion of patients with new CNS lesions at the time of disease progression was 17/143 patients (12%) on the TAGRISSO arm and 26/73 patients (36%) on the placebo arm.

14.3 Previously Untreated EGFR Mutation-Positive Metastatic NSCLC

FLAURA – TAGRISSO Monotherapy

The efficacy of TAGRISSO was demonstrated in a randomized, multicenter, double-blind, active-controlled trial (FLAURA [NCT02296125]) in patients with EGFR exon 19 deletions or exon 21 L858R mutation-positive, metastatic NSCLC, who had not received previous systemic treatment for metastatic disease. Patients were required to have measurable disease per RECIST v1.1, a WHO performance status of 0-1, and EGFR exon 19 deletions or exon 21 L858R mutation in tumor prospectively identified by the cobas® EGFR Mutation Test in a central laboratory or by an investigational assay at a CLIA-certified or accredited laboratory. Patients with CNS metastases not requiring steroids and with stable neurologic status for at least two weeks after completion of definitive surgery or radiotherapy were eligible. Patients were assessed at the investigator’s discretion for CNS metastases if they had a history of, or suspected, CNS metastases at study entry.

Patients were randomized (1:1) to receive TAGRISSO 80 mg orally once daily or to receive gefitinib 250 mg orally once daily or erlotinib 150 mg orally once daily until disease progression or unacceptable toxicity. Randomization was stratified by EGFR mutation type (exon 19 deletions or exon 21 L858R mutation) and ethnicity (Asian or non-Asian). Patients randomized to the control arm were offered TAGRISSO at the time of disease progression if tumor samples tested positive for the EGFR T790M mutation. The major efficacy outcome measure was progression-free survival (PFS), as assessed by investigator. Additional efficacy outcome measures included OS and overall response rate (ORR).

A total of 556 patients were randomized to TAGRISSO (n=279) or to control (gefitinib n=183; erlotinib n=94). The median age was 64 years (range 26-93 years); 54% were <65 years of age; 63% were female; 62% were Asian and 64% were never smokers. Baseline WHO performance status was 0 (41%) or 1 (59%); 5% had Stage IIIb and 95% had Stage IV; and 7% received prior systemic cytotoxic chemotherapy as neoadjuvant or adjuvant therapy. With regard to EGFR tumor testing, 63% were exon 19 deletions and 37% were exon 21 L858R; 5 patients (<1%) also had a concomitant de novo T790M mutation. EGFR mutation status was confirmed centrally using the cobas® EGFR Mutation Test in 90% of patients. At the time of the final data cut-off, of those randomized to TAGRISSO and to investigator’s choice erlotinib or gefitinib arm, 133 (48%) and 180 (65%) patients had received at least one subsequent treatment, respectively. Out of the 180 patients randomized to erlotinib or gefitinib who received subsequent treatment, 85 (47%) patients received TAGRISSO as first subsequent therapy.

FLAURA demonstrated a statistically significant improvement in PFS for patients randomized to TAGRISSO as compared to erlotinib or gefitinib (see Table 16 and Figure 4). The final analysis of overall survival demonstrated a statistically significant improvement in overall survival in patients randomized to TAGRISSO compared to erlotinib or gefitinib (see Table 17 and Figure 5).

Table 16. Efficacy Results in FLAURA according to Investigator Assessment
Efficacy Parameter | TAGRISSO (N=279) | EGFR TKI (gefitinib or erlotinib) (N=277)
Progression-Free Survival (PFS)
PFS events (%) | 136 (49) | 206 (74)
Progressive disease (%) | 125 (45) | 192 (69)
Death [Without documented radiological disease progression.] (%) | 11 (4) | 14 (5)
Median PFS in months (95% CI) | 18.9 (15.2, 21.4) | 10.2 (9.6, 11.1)
Hazard Ratio (95% CI) [Stratified by ethnicity (Asian vs Other races) and mutation status (Ex19del vs L858R).] , [Pike estimator.] | 0.46 (0.37, 0.57)
p-value, [Stratified log-rank test.] | <0.0001
Overall Survival (OS)
Number of deaths (%) | 155 (56) | 166 (60)
Median OS in months (95% CI) | 38.6 (34.5, 41.8) | 31.8 (26.6, 36.0)
Hazard Ratio (95% CI), | 0.80 (0.64, 1.00)
p-value, | 0.0462
Overall Response Rate (ORR) [Confirmed responses.]
ORR, % (95% CI) | 77 (71, 82) | 69 (63, 74)
Complete response, % | 2 | 1
Partial response, % | 75 | 68
Duration of Response (DoR)
Median in months (95% CI) | 17.6 (13.8, 22.0) | 9.6 (8.3, 11.1)

Figure 4. Kaplan-Meier Curves of PFS by Investigator Assessment in FLAURA

In a supportive analysis of PFS according to blinded independent central review (BICR), median PFS was 17.7 months in the TAGRISSO arm compared to 9.7 months in the EGFR TKI comparator arm (HR=0.45; 95% CI: 0.36, 0.57).

Figure 5. Kaplan-Meier Curves of Overall Survival in FLAURA

Of 556 patients, 200 patients (36%) had baseline brain scans reviewed by BICR; this included 106 patients in the TAGRISSO arm and 94 patients in the investigator choice of EGFR TKI arm. Of these 200 patients, 41 had measurable CNS lesions per RECIST v1.1. Results of pre-specified exploratory analyses of CNS ORR and duration of response (DoR) by BICR in the subset of patients with measurable CNS lesions at baseline are summarized in Table 17.

Table 17. CNS ORR and DOR by BICR in Patients with Measurable CNS Lesions at Baseline in FLAURA
 | TAGRISSO; N=22 | EGFR TKI; (gefitinib or erlotinib); N=19
CNS Tumor Response Assessment [According to RECIST v1.1.] [Based on confirmed response.]
CNS ORR, % (95% CI) | 77 (55, 92) | 63 (38, 84)
Complete response, % | 18 | 0
CNS Duration of Response [Based on patients with response only; DoR defined as the time from the date of first documented response (complete response or partial response) until progression or death event.]
Number of responders | 17 | 12
Response Duration ≥6 months, % | 88 | 50
Response Duration ≥12 months, % | 47 | 33

14.4 Previously Untreated EGFR Mutation-Positive Locally Advanced or Metastatic NSCLC

FLAURA2 – TAGRISSO in Combination with Pemetrexed and Platinum-based Chemotherapy

The efficacy of TAGRISSO in combination with pemetrexed and platinum-based chemotherapy was demonstrated in a randomized, multicenter, open-label trial (FLAURA2 [NCT04035486]) in patients with EGFR exon 19 deletion or exon 21 L858R mutation-positive locally advanced or metastatic NSCLC, who had not received previous systemic treatment for advanced disease. Patients were required to have measurable disease per RECIST v1.1, a WHO performance status of 0-1, and EGFR exon 19 deletions or exon 21 L858R mutations as identified by the cobas® EGFR Mutation Test v2 performed prospectively in tissue samples in a central laboratory or by a local test performed in a CLIA-certified or accredited laboratory.

Patients were randomized (1:1) to one of the following treatment arms:

- TAGRISSO (80 mg) orally once daily with pemetrexed (500 mg/m^2) and investigator’s choice of cisplatin (75 mg/m2) or carboplatin (AUC5) administered intravenously on Day 1 of 21-day cycles for 4 cycles, followed by TAGRISSO (80 mg) orally once daily and pemetrexed (500 mg/m^2) administered intravenously every 3 weeks
- TAGRISSO (80 mg) orally once daily

Randomization was stratified by race (Chinese/Asian, Other races except-Chinese/Asian or other races), WHO performance status (0 or 1), and method for tissue testing (central or local). Patients received study therapy until intolerance to therapy, or the investigator determined that the patient was no longer experiencing clinical benefit.

Progression-free survival, as assessed by investigator per RECIST 1.1 was the primary efficacy outcome measure. Overall survival was a key secondary outcome measure. Additional efficacy outcome measures included ORR and DoR.

A total of 557 patients were randomized to either TAGRISSO in combination with pemetrexed and platinum-based chemotherapy (n=279) or TAGRISSO monotherapy (n=278). The median age was 61 years (range 26-85 years); 39% were ≥65 years and 8% were ≥75 years of age; 61% were female; 64% were Asian and 66% were never smokers. Baseline WHO PS was 0 (37%) or 1 (63%); 4% had locally advanced and 96% had metastatic NSCLC; and 1.8% received prior systemic cytotoxic chemotherapy as neoadjuvant or adjuvant therapy. With regard to EGFR tumor testing, 61% of tumors had exon 19 deletions and 38% had exon 21 L858R mutations; 0.7% of patients had tumors with both exon 19 deletions and exon 21 L858R. EGFR mutation status was centrally confirmed using the cobas® EGFR Mutation Test v2 in 96% of patients.

FLAURA2 demonstrated a statistically significant improvement in PFS for patients randomized to TAGRISSO in combination with pemetrexed and platinum-based chemotherapy as compared to TAGRISSO monotherapy (see Table 18 and Figure 6). While OS results were immature at the current analysis, with 45% of pre-specified deaths for the final analysis reported, no trend towards a detriment was observed.

Table 18. Efficacy Results in FLAURA2 according to Investigator Assessment
Efficacy Parameter | TAGRISSO with pemetrexed and platinum-based chemotherapy (N=279) | TAGRISSO (N=278)
Progression-Free Survival (PFS) [PFS and ORR results by BICR were consistent with those reported via investigator assessment.]
PFS events (%) | 120 (43) | 166 (60)
Progressive disease (%) | 95 (34) | 158 (57)
Death [Without documented radiological disease progression] (%) | 25 (9) | 8 (2.9)
Median PFS in months (95% CI) | 25.5 (24.7, NE) | 16.7 (14.1, 21.3)
Hazard Ratio (95% CI) [Stratified by race (Chinese/Asian, -Other races except Chinese/Asian vs other races), WHO performance status (0 or 1) and method of tissue testing (central or local).] [Pike estimator.] | 0.62 (0.49, 0.79)
p-value [Stratified log-rank test.] | <0.0001
Overall Response Rate (ORR) [Confirmed responses.]
ORR, % (95% CI) | 77 (71, 82) | 69 (63, 74)
Complete response, % | 0.4 | 0.4
Partial response, % | 76 | 68
Duration of Response (DoR)
Median in months (95% CI) | 24.9 (22.1, NE) | 17.9 (15.2, 20.9)
NE=Not Estimable; NR=Not Reached

Figure 6. Kaplan-Meier Curves of PFS by Investigator Assessment in FLAURA2

All patients had available baseline brain scans reviewed by BICR using modified RECIST; 78/557 (14%) patients had CNS measurable lesions. Results of pre-specified exploratory analyses of CNS ORR and DoR by BICR are summarized in Table 19.

Table 19. Exploratory Analysis – CNS Efficacy by BICR in Patients with CNS Metastases on a Baseline Brain Scan in FLAURA2
Efficacy Parameter | CNS Measurable Lesions
Efficacy Parameter | TAGRISSO with pemetrexed and platinum-based chemotherapy (N=40) | TAGRISSO (N=38)
CNS Tumor Response Assessment [According to RECIST v1.1.] [Based on confirmed response.]
CNS ORR, % (95% CI) | 80 (64, 91) | 76 (60, 89)
Complete response, % | 48 | 16
Partial response, % | 33 | 61
CNS Duration of Response [Based on patients with response only; DoR defined as the time from the date of first documented response (complete response or partial response) until progression or death event.]
Number of responders | 32 | 29
Response Duration ≥6 months, % | 75 | 50
Response Duration ≥12 months, % | 65 | 34

14.5 Previously Treated EGFR T790M Mutation-Positive Metastatic NSCLC

The efficacy of TAGRISSO was demonstrated in a randomized, multicenter open-label, active-controlled trial in patients with metastatic EGFR T790M mutation-positive NSCLC who had progressed on prior systemic therapy, including an EGFR TKI (AURA3) [NCT02151981]. All patients were required to have EGFR T790M mutation-positive NSCLC identified by the cobas® EGFR Mutation Test performed in a central laboratory prior to randomization.

A total of 419 patients were randomized 2:1 to receive TAGRISSO (n=279) or platinum-based doublet chemotherapy (n=140). Randomization was stratified by ethnicity (Asian vs non-Asian). Patients in the TAGRISSO arm received TAGRISSO 80 mg orally once daily until intolerance to therapy, disease progression, or investigator determination that the patient was no longer benefiting from treatment. Patients in the chemotherapy arm received pemetrexed 500 mg/m^2 with carboplatin AUC5 or pemetrexed 500 mg/m^2 with cisplatin 75 mg/m^2 on Day 1 of every 21-day cycle for up to 6 cycles. Patients whose disease had not progressed after four cycles of platinum-based chemotherapy could have received pemetrexed maintenance therapy (pemetrexed 500 mg/m^2 on Day 1 of every 21-day cycle).

The major efficacy outcome measure was PFS according to Response Evaluation Criteria in Solid Tumors (RECIST v1.1) by investigator assessment. Additional efficacy outcome measures included ORR, DoR, and OS. Patients randomized to the chemotherapy arm who had radiological progression according to both investigator and BICR were permitted to cross over to receive treatment with TAGRISSO.

The baseline demographic and disease characteristics of the overall trial population were: median age 62 years (range: 20-90 years), ≥75 years old (15%), female (64%), White (32%), Asian (65%), never smoker (68%), WHO performance status 0 or 1 (100%). Fifty-four percent (54%) of patients had extra-thoracic visceral metastases, including 34% with central nervous system (CNS) metastases (including 11% with measurable CNS metastases) and 23% with liver metastases. Forty-two percent (42%) of patients had metastatic bone disease.

In AURA3, there was a statistically significant improvement in PFS in the patients randomized to TAGRISSO compared to chemotherapy (see Table 20 and Figure 7). No statistically significant difference was observed between the treatment arms at final OS analysis. At the time of the final OS analysis, 99 patients (71%) randomized to chemotherapy had crossed over to TAGRISSO treatment.

Table 20. Efficacy Results According to Investigator Assessment in AURA3
Efficacy Parameter | TAGRISSO (N=279) | Chemotherapy (N=140)
Progression-Free Survival
Number of events (%) | 140 (50) | 110 (79)
Progressive disease (%) | 129 (46) | 104 (74)
Death [Without documented radiological disease progression.] (%) | 11 (4) | 6 (4)
Median PFS in months (95% CI) | 10.1 (8.3, 12.3) | 4.4 (4.2, 5.6)
Hazard Ratio (95% CI [Stratified by ethnicity (Asian vs other races).] [Pike estimator.]) | 0.30 (0.23,0.41)
p-value [Stratified log-rank test.] | <0.001
Overall Survival
Number of deaths (%) | 188 (67) | 93 (66)
Median OS in months (95% CI) | 26.8 (23.5, 31.5) | 22.5 (20.2, 28.8)
Hazard Ratio (95% CI) | 0.87 (0.67, 1.12)
p-value | 0.277
Overall Response Rate [Confirmed responses.]
ORR, % (95% CI) | 65 (59, 70) | 29 (21, 37)
Complete response, % | 1 | 1
Partial response, % | 63 | 27
p-value [Logistic regression analysis.] | <0.001
Duration of Response (DoR)
Median in months (95% CI) | 11.0 (8.6, 12.6) | 4.2 (3.0, 5.9)

Figure 7. Kaplan-Meier Curves of PFS by Investigator Assessment in AURA3

In a supportive analysis of PFS according to BICR, median PFS was 11 months in the TAGRISSO arm compared to 4.2 months in the chemotherapy arm (HR 0.28; 95% CI: 0.20, 0.38).

Of 419 patients, 205 (49%) had baseline brain scans reviewed by BICR; this included 134 (48%) patients in the TAGRISSO arm and 71 (51%) patients in the chemotherapy arm. Assessment of CNS efficacy by RECIST v1.1 was performed in the subgroup of 46/419 (11%) patients identified by BICR to have measurable CNS lesions on a baseline brain scan. Results are summarized in Table 21.

Table 21. CNS ORR and DoR by BICR in Patients with Measurable CNS Lesions at Baseline in AURA3
 | TAGRISSO; N=30 | Chemotherapy; N=16
CNS Tumor Response Assessment [According to RECIST v 1.1.] [Based on confirmed response.]
CNS ORR, % (95% CI) | 57 (37, 75) | 25 (7, 52)
Complete response, % | 7 | 0
Duration of CNS Response [Based on patients with response only; DoR defined as the time from the date of first documented response (complete response or partial response) until progression or death event.]
Number of responders | 17 | 4
Response Duration ≥6 months, % | 47 | 0
Response Duration ≥9 months, % | 12 | 0

16 HOW SUPPLIED/STORAGE AND HANDLING

80 mg tablets: beige, oval and biconvex tablet marked with “AZ 80” on one side and plain on the reverse and are available in bottles of 30 (NDC 0310-1350-30).

40 mg tablets: beige, round and biconvex tablet marked with “AZ 40” on one side and plain on the reverse and are available in bottles of 30 (NDC 0310-1349-30).

Store TAGRISSO bottles at 25°C (77°F). Excursions permitted to 15-30°C (59-86°F) [see USP Controlled Room Temperature].

17 PATIENT COUNSELING INFORMATION

Advise the patient to read the FDA-approved patient labeling (Patient Information).

Interstitial Lung Disease/Pneumonitis

- Inform patients of the risks of severe or fatal ILD, including pneumonitis. Advise patients to contact their healthcare provider immediately to report new or worsening respiratory symptoms [see Error! Hyperlink reference not valid.].

QTc Interval Prolongation

- Inform patients of symptoms that may be indicative of significant QTc prolongation including dizziness, lightheadedness, and syncope. Advise patients to report these symptoms and to inform their physician about the use of any heart or blood pressure medications [see Error! Hyperlink reference not valid.].

Cardiomyopathy

- Inform patients that TAGRISSO can cause cardiomyopathy. Advise patients to immediately report any signs or symptoms of heart failure to their healthcare provider [see Error! Hyperlink reference not valid.].

Keratitis

- Advise patients to contact their healthcare provider immediately if they develop eye symptoms (eye inflammation, lacrimation, light sensitivity, eye pain, red eye or changes in vision) [see Error! Hyperlink reference not valid.].

Erythema Multiforme Major, Stevens-Johnson Syndrome, and Toxic Epidermal Necrolysis

- Inform patients of signs and symptoms that may be indicative of EMM, SJS, or TEN. Advise patients to contact their healthcare provider immediately if they develop target lesions or severe blistering or peeling of skin [see Error! Hyperlink reference not valid.].

Cutaneous Vasculitis

- Inform patients of signs and symptoms that may be indicative of cutaneous vasculitis. Advise patients to contact their healthcare provider immediately if they develop multiple, non-blanching red papules on their forearms, lower legs, or buttocks or large hives on their trunk that do not go away within 24 hours and develop a bruised appearance [see Error! Hyperlink reference not valid.].

Aplastic Anemia

- Inform patients of signs and symptoms of aplastic anemia including but not limited to new or persistent fevers, bruising, bleeding, pallor, infection, tiredness or weakness. Advise patients to contact their healthcare provider immediately if signs and symptoms suggestive of aplastic anemia develop [see Error! Hyperlink reference not valid.].

Embryo-Fetal Toxicity

- Advise pregnant women and females of reproductive potential of the potential risk to a fetus. Advise females to inform their healthcare provider if they become pregnant or if pregnancy is suspected, while taking TAGRISSO [see Error! Hyperlink reference not valid. and Use in Specific Populations (8.1)].

Females and Males of Reproductive Potential

- Advise females of reproductive potential to use effective contraception during treatment with TAGRISSO and for 6 weeks after the last dose [see Use in Specific Populations (8.3)].
- Advise males to use effective contraception during treatment and for 4 months after the last dose of TAGRISSO [see Use in Specific Populations (8.3)].

Lactation

- Advise women not to breastfeed during treatment with TAGRISSO and for 2 weeks after the last dose [see Use in Specific Populations (8.2)].

Distributed by:
AstraZeneca Pharmaceuticals LP
Wilmington, DE 19850

TAGRISSO is a registered trademark of the AstraZeneca group of companies.

This Patient Information has been approved by the U.S. Food and Drug Administration. Revised: 09/2024

©AstraZeneca 2024

Patient Medication Information

PATIENT INFORMATION
TAGRISSO®(tuh-GRISS-oh)
(osimertinib)
tablets

What is the most important information I should know about TAGRISSO?

TAGRISSO may cause serious side effects, including:

- Lung problems. TAGRISSO may cause severe lung problems that may lead to death. Symptoms may be similar to those symptoms from lung cancer. Tell your healthcare provider right away if you have any new or worsening lung symptoms, including trouble breathing, shortness of breath, cough, or fever.
- Heart problems, including heart failure. TAGRISSO may cause heart problems that may lead to death. Your healthcare provider should check your heart function before you start taking TAGRISSO and during treatment as needed. Tell your healthcare provider right away if you have any of the following signs and symptoms of a heart problem: feeling like your heart is pounding or racing, shortness of breath, swelling of your ankles and feet, dizziness, feeling lightheaded, or feeling faint.
- Eye problems. TAGRISSO may cause eye problems. Tell your healthcare provider right away if you have symptoms of eye problems which may include watery eyes, sensitivity to light, eye pain, eye redness, or vision changes. Your healthcare provider may send you to see an eye specialist (ophthalmologist) if you get eye problems with TAGRISSO.
- Skin problems. TAGRISSO may cause skin problems. Tell your healthcare provider right away if you develop skin reactions that look like rings (target lesions), severe blistering or peeling of the skin.
- Inflammation of the blood vessels in your skin. TAGRISSO may cause blood vessel problems in your skin. Tell your healthcare provider right away if you develop purple spots or redness of the skin that does not fade in color when pressed (non-blanching) on your lower arms, lower legs, or buttocks or large hives on the main part of your body (trunk) that do not go away within 24 hours and look bruised.

Blood and bone marrow problems. TAGRISSO may cause a condition where your bone marrow cannot make enough new blood cells (aplastic anemia), and which may lead to death. Your healthcare provider will monitor your blood cell counts before you start and during treatment with TAGRISSO. Tell your healthcare provider right away if you develop any signs or symptoms of blood and bone marrow problems, including:

- a new fever or fever that does not go away (temperature 100.4°F or higher)

- easy bruising or bleeding that will not stop
- unusually pale skin

- infection
- tiredness
- weakness

See “What are the possible side effects of TAGRISSO?” for more information about side effects.

What is TAGRISSO?

TAGRISSO is a prescription medicine used to treat adults with non-small cell lung cancer (NSCLC) that has certain abnormal epidermal growth factor receptor (EGFR) gene(s):

- to help prevent your lung cancer from coming back after your tumor(s) has been removed by surgery, or
- when your lung cancer has spread to nearby tissues (locally advanced) that is unable to be removed (unresectable) by surgery and has responded or stabilized following chemotherapy and radiation treatment, or
- as your first treatment when your lung cancer has spread to other parts of the body (metastatic), or
- in combination with pemetrexed and platinum-based chemotherapy, as your first treatment when your lung cancer has spread to nearby tissues (locally advanced) or to other parts of the body (metastatic).
- when your lung cancer has spread to other parts of the body (metastatic), and you have had previous treatment with an EGFR tyrosine kinase inhibitor (TKI) medicine that did not work or is no longer working.

Your healthcare provider will perform a test to make sure that TAGRISSO is right for you.

It is not known if TAGRISSO is safe and effective in children.

Before taking TAGRISSO, tell your healthcare provider about all of your medical conditions, including if you:

- have lung or breathing problems other than your lung cancer.
- have heart problems, including a condition called long QTc syndrome.
- have problems with your electrolytes, such as sodium, potassium, calcium, or magnesium.
- have a history of eye problems.
- are pregnant or plan to become pregnant. TAGRISSO can harm your unborn baby. Tell your healthcare provider right away if you become pregnant during treatment with TAGRISSO or think you may be pregnant.
- Females who are able to become pregnant should have a pregnancy test before starting treatment with TAGRISSO. You should use effective birth control (contraception) during treatment with TAGRISSO and for 6 weeks after the last dose of TAGRISSO.
- Males who have female partners that are able to become pregnant should use effective birth control during treatment with TAGRISSO and for 4 months after the last dose of TAGRISSO.
- are breastfeeding or plan to breastfeed. It is not known if TAGRISSO passes into your breast milk. Do not breastfeed during treatment with TAGRISSO and for 2 weeks after your last dose of TAGRISSO. Talk to your healthcare provider about the best way to feed your baby during this time.

Tell your healthcare provider about all the medicines you take, including prescription and over-the-counter medicines, vitamins, or herbal supplements. Especially tell your healthcare provider if you take a heart or blood pressure medicine.

Before taking TAGRISSO, tell your healthcare provider about all of your medical conditions, including if you:

- have lung or breathing problems other than your lung cancer.
- have heart problems, including a condition called long QTc syndrome.
- have problems with your electrolytes, such as sodium, potassium, calcium, or magnesium.
- have a history of eye problems.
- are pregnant or plan to become pregnant. TAGRISSO can harm your unborn baby. Tell your healthcare provider right away if you become pregnant during treatment with TAGRISSO or think you may be pregnant.
- Females who are able to become pregnant should have a pregnancy test before starting treatment with TAGRISSO. You should use effective birth control (contraception) during treatment with TAGRISSO and for 6 weeks after the last dose of TAGRISSO.
- Males who have female partners that are able to become pregnant should use effective birth control during treatment with TAGRISSO and for 4 months after the last dose of TAGRISSO.
- are breastfeeding or plan to breastfeed. It is not known if TAGRISSO passes into your breast milk. Do not breastfeed during treatment with TAGRISSO and for 2 weeks after your last dose of TAGRISSO. Talk to your healthcare provider about the best way to feed your baby during this time.

Tell your healthcare provider about all the medicines you take, including prescription and over-the-counter medicines, vitamins, or herbal supplements. Especially tell your healthcare provider if you take a heart or blood pressure medicine.

How should I take TAGRISSO?

- Take TAGRISSO exactly as your healthcare provider tells you to take it.
- Your healthcare provider may change your dose, temporarily stop, or permanently stop treatment with TAGRISSO if you have side effects.
- Take TAGRISSO 1 time each day.
- You can take TAGRISSO with or without food.
- If you miss a dose of TAGRISSO, do not make up for the missed dose. Take your next dose at your regular time.
- If you cannot swallow TAGRISSO tablets whole:
- Place your dose of TAGRISSO in a container that contains 60 mL (2 ounces) of water. Do not use carbonated water or any other liquids.
- Stir the TAGRISSO tablet and water until the TAGRISSO tablet is in small pieces (the tablet will not completely dissolve). Do not crush, heat, or use ultrasound to prepare the mixture.
- Drink the TAGRISSO and water mixture right away.
- Add 120 mL to 240 mL (4 to 8 ounces) of water into the container and drink to make sure that you take your full dose of TAGRISSO.
- If you have a nasogastric (NG) tube:
- Follow the same instructions for mixing TAGRISSO tablets in a container that contains 15 mL of water. Do not use carbonated water or any other liquids.
- Stir the TAGRISSO tablets and water until the TAGRISSO tablets are in small pieces (the tablets will not completely dissolve). Do not crush, heat, or use ultrasound to prepare the mixture.
- Add another 15 mL of water into the container to make sure no pieces of TAGRISSO tablet remain.
- Give the TAGRISSO tablet and water mixture using the NG tube manufacturer instructions within 30 minutes.

Add another 30 mL of water into the syringe and give the water and any remaining TAGRISSO through the NG tube to make sure that all of the medicine is given. Repeat this step until no pieces remain in the syringe. This will help to ensure that the full prescribed dose of the TAGRISSO is given.

What are the possible side effects of TAGRISSO?

TAGRISSO may cause serious side effects:

• See “What is the most important information I should know about TAGRISSO?”

The most common side effects of TAGRISSO when given alone include:

low white blood cell counts

low platelet counts

low red blood cell counts (anemia)

diarrhea

rash

muscle, bone, or joint pain

changes in your nails, including: redness, tenderness, pain, inflammation, brittleness, separation from the nailbed, and shedding of nail

dry skin

mouth sores

tiredness

The most common side effects of TAGRISSO when given alone after treatment with platinum-based chemotherapy and radiation treatment include:

low white blood cell counts

lung problems

low platelet counts

rash

diarrhea

changes in your nails, including: redness, tenderness, pain, inflammation, brittleness, separation from the nailbed, and shedding of nail

Cough

COVID-19

The most common side effects of TAGRISSO in combination with pemetrexed and platinum-based chemotherapy include:

low white blood cell counts

low platelet counts

rash

diarrhea

mouth sores

changes in your nails, including: redness, tenderness, pain, inflammation, brittleness, separation from the nailbed, and shedding of nail

dry skin

increase of a substance in the blood called creatinine

Tell your healthcare provider if you have any side effect that bothers you or that does not go away.

These are not all the possible side effects of TAGRISSO. For more information, ask your healthcare provider or pharmacist.

Call your doctor for medical advice about side effects. You may report side effects to FDA at 1-800-FDA-1088.

How should I store TAGRISSO?

- Store TAGRISSO at room temperature between 68°F to 77°F (20°C to 25°C).
- Safely throw away medicine that is out of date or that you no longer need.

Keep TAGRISSO and all medicines out of the reach of children.

General information about the safe and effective use of TAGRISSO.

Medicines are sometimes prescribed for purposes other than those listed in a Patient Information leaflet. Do not use TAGRISSO for a condition for which it was not prescribed. Do not give TAGRISSO to other people, even if they have the same symptoms you have. It may harm them. You can ask your pharmacist or healthcare provider for information about TAGRISSO that is written for health professionals.

What are the ingredients in TAGRISSO?

Active ingredient: osimertinib

Inactive ingredients: mannitol, microcrystalline cellulose, low-substituted hydroxypropyl cellulose, and sodium stearyl fumarate. Tablet coating contains: polyvinyl alcohol, titanium dioxide, macrogol 3350, talc, ferric oxide yellow, ferric oxide red and ferric oxide black.

Distributed by: AstraZeneca Pharmaceuticals LP, Wilmington, DE 19850

© AstraZeneca 2024

For more information, go to www.Tagrisso.com or call 1-800-236-9933.

This Patient Information has been approved by the U.S. Food and Drug Administration. Revised: 09/2024

PACKAGE/LABEL PRINCIPAL DISPLAY PANEL – 40 mg

NDC 0310-1349-30 30 Tablets

Tagrisso®

(osimertinib) tablets

40 mg per tablet

Rx only

AstraZeneca

PACKAGE/LABEL PRINCIPAL DISPLAY PANEL – 80 mg

NDC 0310-1350-30 30 Tablets

Tagrisso®

(osimertinib) tablets

80 mg per tablet

Rx only

AstraZeneca

PACKAGE/LABEL PRINCIPAL DISPLAY PANEL

NDC 0310-1248-30 30 Tablets

Tagrisso®

(osimertinib) tablets

40 mg per tablet

Rx only

AstraZeneca

PACKAGE/LABEL PRINCIPAL DISPLAY PANEL

NDC 0310-1251-30 30 Tablets

Tagrisso®

(osimertinib) tablets

80 mg per tablet

Rx only

AstraZeneca